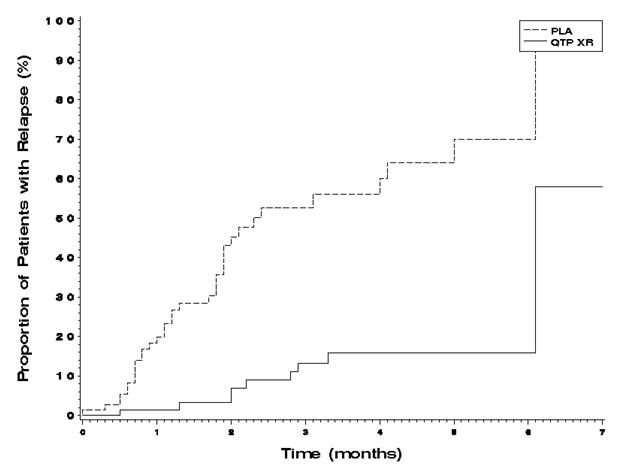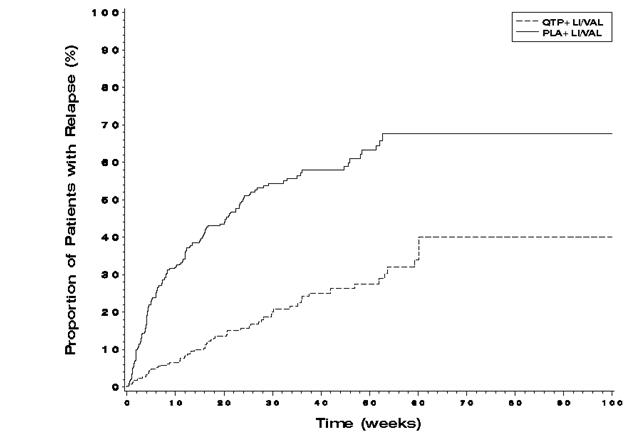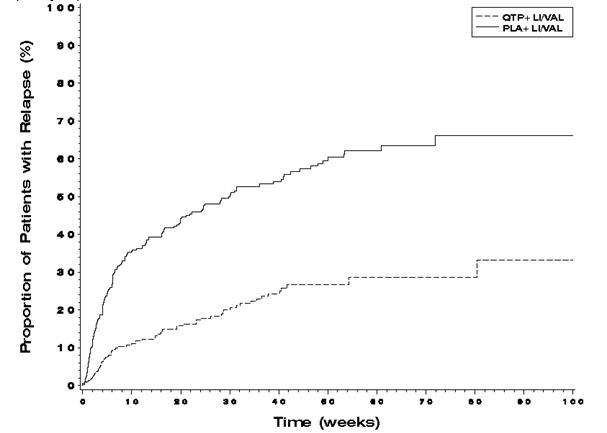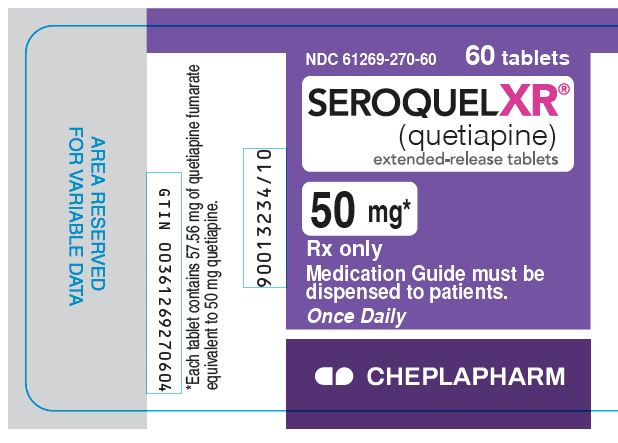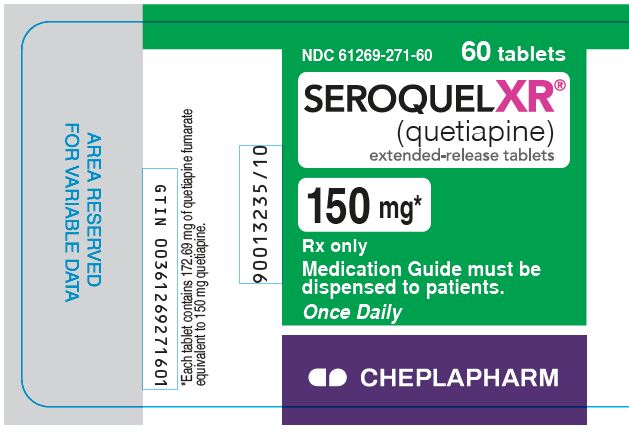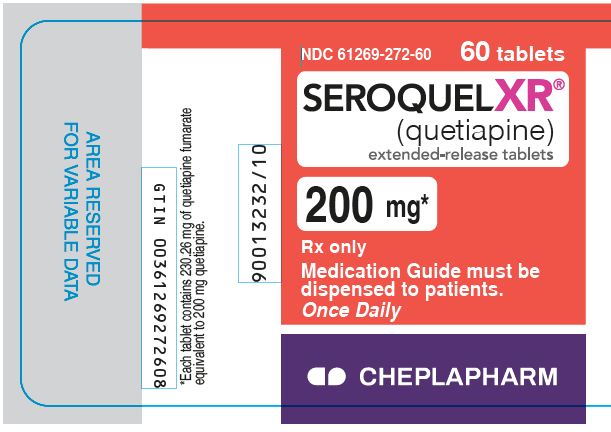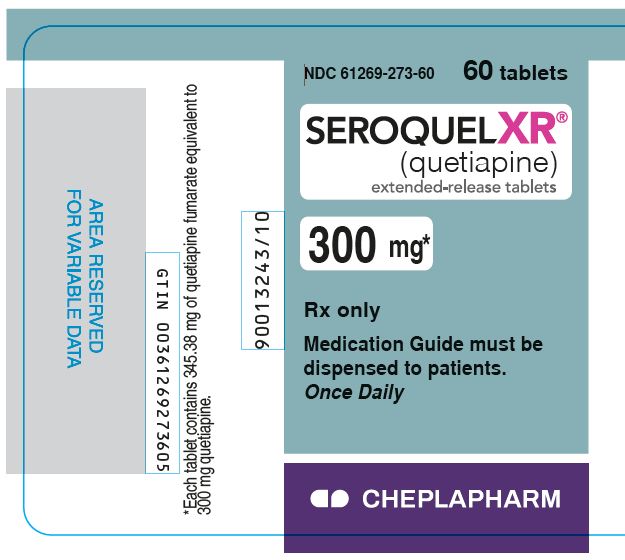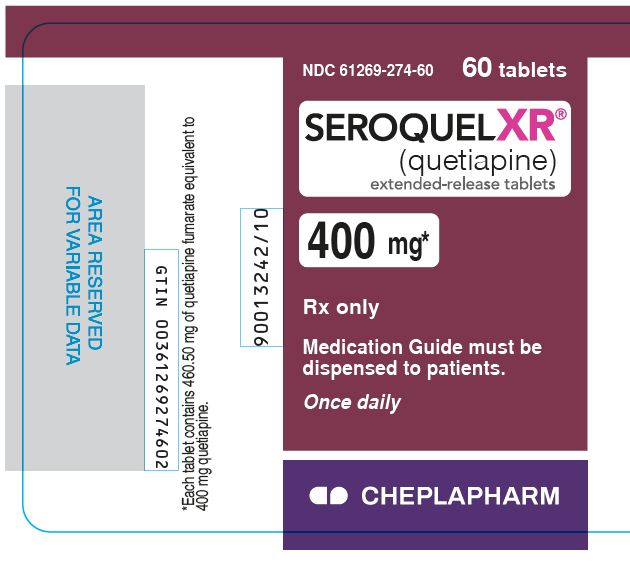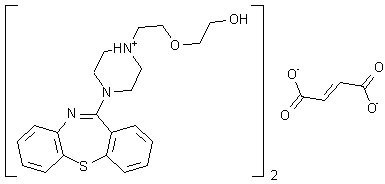 DRUG LABEL: SEROQUEL
NDC: 61269-272 | Form: TABLET, EXTENDED RELEASE
Manufacturer: H2-Pharma, LLC
Category: prescription | Type: HUMAN PRESCRIPTION DRUG LABEL
Date: 20250613

ACTIVE INGREDIENTS: QUETIAPINE FUMARATE 200 mg/1 1
INACTIVE INGREDIENTS: LACTOSE MONOHYDRATE; MICROCRYSTALLINE CELLULOSE; SODIUM CITRATE, UNSPECIFIED FORM; HYPROMELLOSE, UNSPECIFIED; MAGNESIUM STEARATE; FERRIC OXIDE YELLOW; POLYETHYLENE GLYCOL 400; TITANIUM DIOXIDE; WATER

HIGHLIGHTS OF PRESCRIBING INFORMATION

These highlights do not include all the information needed to use SEROQUEL XR safely and effectively. See full prescribing information for SEROQUEL XR.
SEROQUEL XR® (quetiapine) extended-release tablets, for oral use
Initial U.S. Approval: 1997

RECENT MAJOR CHANGES

WARNINGS AND PRECAUTIONS (5.15) 4/2025

WARNING: INCREASED MORTALITY IN ELDERLY PATIENTS WITH DEMENTIA-RELATED PSYCHOSIS; and SUICIDAL THOUGHTS AND BEHAVIORS

See full prescribing information for complete boxed warning.

Increased Mortality in Elderly Patients with Dementia-Related Psychosis

•Elderly patients with dementia-related psychosis treated with antipsychotic drugs are at an increased risk of death. SEROQUEL XR is not approved for elderly patients with dementia-related psychosis. (5.1)

Suicidal Thoughts and Behaviors

•Increased risk of suicidal thoughts and behavior in children, adolescents and young adults taking antidepressants. (5.2)•Monitor for worsening and emergence of suicidal thoughts and behaviors. (5.2)

1 INDICATIONS AND USAGE

SEROQUEL XR is an atypical antipsychotic indicated for the treatment of:

- Schizophrenia (1.1)
- Bipolar I disorder, manic, or mixed episodes (1.2)
- Bipolar disorder, depressive episodes (1.2)
- Major depressive disorder, adjunctive therapy with antidepressants (1.3)

2 DOSAGE AND ADMINISTRATION

- Swallow tablets whole and do not split, chew or crush (2.1)
- Take without food or with a light meal (approx. 300 calories) (2.1)
- Administer once daily, preferably in the evening (2.1)
- Geriatric Use: Consider a lower starting dose (50 mg/day), slower titration, and careful monitoring during the initial dosing period in the elderly (2.3, 8.5)
- Hepatic Impairment: Lower starting dose (50 mg/day) and slower titration may be needed (2.4, 8.7, 12.3)

Indication | Initial Dose | Recommended Dose | Maximum Dose
Schizophrenia - Adults (2.2) | 300 mg/day | 400-800 mg/day | 800 mg/day
Schizophrenia - Adolescents (13 to 17 years) (2.2) | 50 mg/day | 400-800 mg/day | 800 mg/day
Bipolar I Disorder manic or mixed - Acute monotherapy or adjunct to lithium or divalproex - Adults (2.2) | 300 mg/day | 400-800 mg/day | 800 mg/day
Bipolar I Disorder, manic Acute monotherapy - Children and Adolescents (10 to 17 years) (2.2) | 50 mg/day | 400-600 mg/day | 600 mg/day
Bipolar Disorder, Depressive Episodes - Adults (2.2) | 50 mg/day | 300 mg/day | 300 mg/day
Major Depressive Disorder, Adjunctive Therapy with Antidepressants - Adults (2.2) | 50 mg/day | 150-300 mg/day | 300 mg/day

3 DOSAGE FORMS AND STRENGTHS

Extended-Release Tablets: 50 mg, 150 mg, 200 mg, 300 mg, and 400 mg (3)

4 CONTRAINDICATIONS

Known hypersensitivity to SEROQUEL XR or any components in the formulation. (4)

5 WARNINGS AND PRECAUTIONS

- Cerebrovascular Adverse Reactions: Increased incidence of cerebrovascular adverse reactions (e.g., stroke, transient ischemic attack) has been seen in elderly patients with dementia-related psychoses treated with atypical antipsychotic drugs (5.3)
- Neuroleptic Malignant Syndrome (NMS): Manage with immediate discontinuation and close monitoring (5.4)
- Metabolic Changes: Atypical antipsychotics have been associated with metabolic changes. These metabolic changes include hyperglycemia, dyslipidemia, and weight gain (5.5)
  ∘ Hyperglycemia and Diabetes Mellitus: Monitor patients for symptoms of hyperglycemia including polydipsia, polyuria, polyphagia, and weakness. Monitor glucose regularly in patients with diabetes or at risk for diabetes
  ∘ Dyslipidemia: Undesirable alterations have been observed in patients treated with atypical antipsychotics. Appropriate clinical monitoring is recommended, including fasting blood lipid testing at the beginning of, and periodically, during treatment
  ∘ Weight Gain: Gain in body weight has been observed; clinical monitoring of weight is recommended
- Tardive Dyskinesia: Discontinue if clinically appropriate (5.6)
- Hypotension: Use with caution in patients with known cardiovascular or cerebrovascular disease (5.7)
- Increased Blood Pressure in Children and Adolescents: Monitor blood pressure at the beginning of, and periodically during treatment in children and adolescents (5.9)
- Leukopenia, Neutropenia, and Agranulocytosis: Monitor complete blood count frequently during the first few months of treatment in patients with a pre-existing low white cell count or a history of leukopenia/neutropenia and discontinue SEROQUEL XR at the first sign of a decline in WBC in absence of other causative factors (5.10)
- Cataracts: Lens changes have been observed in patients during long-term quetiapine treatment. Lens examination is recommended when starting treatment and at 6-month intervals during chronic treatment (5.11)
- Anticholinergic (antimuscarinic) Effects: Use with caution with other anticholinergic drugs and in patients with urinary retention, prostatic hypertrophy, or constipation (5.20)

6 ADVERSE REACTIONS

Most common adverse reactions (incidence ≥5% and twice placebo):

Adults: somnolence, dry mouth, constipation, dizziness, increased appetite, dyspepsia, weight gain, fatigue, dysarthria, and nasal congestion (6.1)

Children and Adolescents: somnolence, dizziness, fatigue, increased appetite, nausea, vomiting, dry mouth, tachycardia, weight increased (6.1)

To report SUSPECTED ADVERSE REACTIONS, contact H2-Pharma at 1-888-864-2308 or FDA at 1-800-FDA-1088 or www.fda.gov/medwatch.

7 DRUG INTERACTIONS

- Concomitant use of strong CYP3A4 inhibitors: Reduce quetiapine dose to one‑sixth when coadministered with strong CYP3A4 inhibitors (e.g., ketoconazole, ritonavir) (2.5, 7.1, 12.3)
- Concomitant use of strong CYP3A4 inducers: Increase quetiapine dose up to 5 fold when used in combination with a chronic treatment (more than 7-14 days) of potent CYP3A4 inducers (e.g., phenytoin, rifampin, St. John’s wort) (2.6, 7.1, 12.3)
- Discontinuation of strong CYP3A4 inducers: Reduce quetiapine dose by 5‑fold within 7-14 days of discontinuation of CYP3A4 inducers (2.6, 7.1, 12.3)

8 USE IN SPECIFIC POPULATIONS

- Pregnancy: May cause extrapyramidal and/or withdrawal symptoms in neonates with third trimester exposure. (8.1)

FULL PRESCRIBING INFORMATION

WARNING: INCREASED MORTALITY IN ELDERLY PATIENTS WITH DEMENTIA-RELATED PSYCHOSIS; and SUICIDAL THOUGHTS AND BEHAVIORS

Increased Mortality in Elderly Patients with Dementia-Related Psychosis

Elderly patients with dementia-related psychosis treated with antipsychotic drugs are at an increased risk of death [see Warnings and Precautions (5.1)]. SEROQUEL XR is not approved for the treatment of patients with dementia-related psychosis [see Warnings and Precautions (5.1)].

Suicidal Thoughts and Behaviors

Antidepressants increased the risk of suicidal thoughts and behavior in children, adolescents, and young adults in short-term studies. These studies did not show an increase in the risk of suicidal thoughts and behavior with antidepressant use in patients over age 24; there was a reduction in risk with antidepressant use in patients aged 65 and older [see Warnings and Precautions (5.2)].

In patients of all ages who are started on antidepressant therapy, monitor closely for worsening, and for emergence of suicidal thoughts and behaviors. Advise families and caregivers of the need for close observation and communication with the prescriber [see Warnings and Precautions (5.2)].

SEROQUEL XR is not approved for use in pediatric patients under ten years of age [see Use in Specific Populations (8.4)].

1 INDICATIONS AND USAGE

1.1 Schizophrenia

SEROQUEL XR is indicated for the treatment of schizophrenia. The efficacy of SEROQUEL XR in schizophrenia was established in one 6-week and one maintenance trial in adults with schizophrenia. Efficacy was supported by three 6-week trials in adults with schizophrenia and one 6-week trial in adolescents with schizophrenia (13-17 years) treated with SEROQUEL [see Clinical Studies (14.1)].

1.2 Bipolar Disorder

SEROQUEL XR is indicated for the acute treatment of manic or mixed episodes associated with bipolar I disorder, both as monotherapy and as an adjunct to lithium or divalproex. The efficacy of SEROQUEL XR in manic or mixed episodes of bipolar I disorder was established in one 3-week trial in adults with manic or mixed episodes associated with bipolar I disorder. Efficacy was supported by two 12-week monotherapy trials and one 3-week adjunctive trial in adults with manic episodes associated with bipolar I disorder as well as one 3-week monotherapy trial in children and adolescents (10 - 17 years) with manic episodes associated with bipolar I disorder treated with SEROQUEL [see Clinical Studies (14.2)].

SEROQUEL XR is indicated for the acute treatment of depressive episodes associated with bipolar disorder. The efficacy of SEROQUEL XR was established in one 8-week trial in adults with bipolar I or II disorder and supported by two 8-week trials in adults with bipolar I or II disorder treated with SEROQUEL [see Clinical Studies (14.2)].

SEROQUEL XR is indicated for the maintenance treatment of bipolar I disorder, as an adjunct to lithium or divalproex. Efficacy was extrapolated from two maintenance trials in adults with bipolar I disorder treated with SEROQUEL. The effectiveness of monotherapy for the maintenance treatment of bipolar I disorder has not been systematically evaluated in controlled clinical trials [see Clinical Studies (14.2)].

1.3 Adjunctive Treatment of Major Depressive Disorder (MDD)

SEROQUEL XR is indicated for use as adjunctive therapy to antidepressants for the treatment of MDD. The efficacy of SEROQUEL XR as adjunctive therapy to antidepressants in MDD was established in two 6-week trials in adults with MDD who had an inadequate response to antidepressant treatment [see Clinical Studies (14.3)].

1.4 Special Considerations in Treating Pediatric Schizophrenia and Bipolar I Disorder

Pediatric schizophrenia and bipolar I disorder are serious mental disorders, however, diagnosis can be challenging. For pediatric schizophrenia, symptom profiles can be variable, and for bipolar I disorder, patients may have variable patterns of periodicity of manic or mixed symptoms. It is recommended that medication therapy for pediatric schizophrenia and bipolar I disorder be initiated only after a thorough diagnostic evaluation has been performed and careful consideration given to the risks associated with medication treatment. Medication treatment for both pediatric schizophrenia and bipolar I disorder is indicated as part of a total treatment program that often includes psychological, educational and social interventions.

2 DOSAGE AND ADMINISTRATION

2.1 Important Administration Instructions

SEROQUEL XR tablets should be swallowed whole and not split, chewed, or crushed.

It is recommended that SEROQUEL XR be taken without food or with a light meal (approximately 300 calories) [see Clinical Pharmacology (12.3)].

SEROQUEL XR should be administered once daily, preferably in the evening.

2.2 Recommended Dosing

The recommended initial dose, titration, dose range and maximum SEROQUEL XR dose for each approved indication is displayed in Table 1 below. After initial dosing, adjustments can be made upwards or downwards, if necessary, depending upon the clinical response and tolerability of the patient [see Clinical Studies (14.1, 14.2 and 14.3)].

Table 1: Recommended Dosing for SEROQUEL XR
Indication | Initial Dose and Titration | Recommended Dose | Maximum Dose
Schizophrenia - Adults | Day 1: 300 mg/day; Dose increases can be made at intervals as short as 1 day and in increments of up to 300 mg/day | 400-800 mg/day | 800 mg/day
Schizophrenia - Adolescents (13 to 17 years) | Day 1: 50 mg/day; Day 2: 100 mg/day; Day 3: 200 mg/day; Day 4: 300 mg/day; Day 5: 400 mg/day | 400-800 mg/day | 800 mg/day
Schizophrenia Maintenance - Monotherapy - Adults | Not applicable | 400-800 mg/day | 800 mg/day
Bipolar I Disorder manic or mixed - Acute monotherapy or adjunct to lithium or divalproex - Adults | Day 1: 300 mg/day; Day 2: 600 mg/day; Day 3: between 400 and 800 mg/day | 400-800 mg/day | 800 mg/day
Bipolar I Disorder, manic - Acute monotherapy - Children and Adolescents (10 to 17 years) | Day 1: 50 mg/day; Day 2: 100 mg/day; Day 3: 200 mg/day; Day 4: 300 mg/day; Day 5: 400 mg/day | 400-600 mg/day | 600 mg/day
Bipolar Disorder, Depressive Episodes - Adults | Day 1: 50 mg/day; Day 2: 100 mg/day; Day 3: 200 mg/day; Day 4: 300 mg/day | 300 mg/day | 300 mg/day
Bipolar I Disorder Maintenance - Adjunct to lithium or divalproex - Adults | Not applicable | 400-800 mg/day | 800 mg/day
Major Depressive Disorder - Adjunctive Therapy with Antidepressants - Adults | Day 1: 50 mg/day; Day 2: 50 mg/day; Day 3: 150 mg/day | 150-300 mg/day | 300 mg/day

Maintenance Treatment for Schizophrenia and Bipolar I Disorder

Maintenance Treatment—Patients should be periodically reassessed to determine the need for maintenance treatment and the appropriate dose for such treatment [see Clinical Studies (14.1, 14.2)].

2.3 Dose Modifications in Elderly Patients

Consideration should be given to a slower rate of dose titration and a lower target dose in the elderly and in patients who are debilitated or who have a predisposition to hypotensive reactions [see Use in Specific Populations (8.5, 8.7), and Clinical Pharmacology (12.3)]. When indicated, dose escalation should be performed with caution in these patients.

Elderly patients should be started on SEROQUEL XR 50 mg/day and the dose can be increased in increments of 50 mg/day depending on the clinical response and tolerability of the individual patient.

2.4 Dose Modifications in Hepatically Impaired Patients

Patients with hepatic impairment should be started on SEROQUEL XR 50 mg/day. The dose can be increased daily in increments of 50 mg/day to an effective dose, depending on the clinical response and tolerability of the patient.

2.5 Dose Modifications when used with CYP3A4 Inhibitors

SEROQUEL XR dose should be reduced to one‑sixth of original dose when co-medicated with a potent CYP3A4 inhibitor (e.g., ketoconazole, itraconazole, indinavir, ritonavir, nefazodone, etc.). When the CYP3A4 inhibitor is discontinued, the dose of SEROQUEL XR should be increased by 6-fold [see Clinical Pharmacology (12.3) and Drug Interactions (7.1)].

2.6 Dose Modifications when used with CYP3A4 Inducers

SEROQUEL XR dose should be increased up to 5-fold of the original dose when used in combination with a chronic treatment (e.g., greater than 7-14 days) of a potent CYP3A4 inducer (e.g., phenytoin, carbamazepine, rifampin, avasimibe, St. John’s wort etc.). The dose should be titrated based on the clinical response and tolerance of the individual patient. When the CYP3A4 inducer is discontinued, the dose of SEROQUEL XR should be reduced to the original level within 7-14 days [see Clinical Pharmacology (12.3) and Drug Interactions (7.1)].

2.7 Re-initiation of Treatment in Patients Previously Discontinued

Although there are no data to specifically address re-initiation of treatment, it is recommended that when restarting therapy of patients who have been off SEROQUEL XR for more than one-week, the initial dosing schedule should be followed. When restarting patients who have been off SEROQUEL XR for less than one-week, gradual dose escalation may not be required and the maintenance dose may be re-initiated.

2.8 Switching Patients from SEROQUEL Tablets to SEROQUEL XR Tablets

Patients who are currently being treated with SEROQUEL (immediate release formulation) may be switched to SEROQUEL XR at the equivalent total daily dose taken once daily. Individual dosage adjustments may be necessary.

2.9 Switching from Antipsychotics

There are no systematically collected data to specifically address switching patients from other antipsychotics to SEROQUEL XR, or concerning concomitant administration with other antipsychotics. While immediate discontinuation of the previous antipsychotic treatment may be acceptable for some patients, more gradual discontinuation may be most appropriate for others. In all cases, the period of overlapping antipsychotic administration should be minimized. When switching patients from depot antipsychotics, if medically appropriate, initiate SEROQUEL XR therapy in place of the next scheduled injection. The need for continuing existing extrapyramidal syndrome medication should be re-evaluated periodically.

3 DOSAGE FORMS AND STRENGTHS

- 50 mg extended-release tablets are peach, film-coated, capsule-shaped, biconvex, intagliated tablet with “XR 50” on one side and plain on the other side
- 150 mg extended-release tablets are white, film-coated, capsule-shaped, biconvex, intagliated tablet with “XR 150” on one side and plain on the other side
- 200 mg extended-release tablets are yellow, film-coated, capsule-shaped, biconvex, intagliated tablet with “XR 200” on one side and plain on the other side
- 300 mg extended-release tablets are pale yellow, film-coated, capsule-shaped, biconvex, intagliated tablet with “XR 300” on one side and plain on the other side
- 400 mg extended-release tablets are white, film-coated, capsule-shaped, biconvex, intagliated tablet with “XR 400” on one side and plain on the other side

4 CONTRAINDICATIONS

Hypersensitivity to quetiapine or to any excipients in the SEROQUEL XR formulation. Anaphylactic reactions have been reported in patients treated with SEROQUEL XR.

5 WARNINGS AND PRECAUTIONS

5.1 Increased Mortality in Elderly Patients with Dementia-Related Psychosis

Elderly patients with dementia-related psychosis treated with antipsychotic drugs are at an increased risk of death. Analysis of 17 placebo-controlled trials (modal duration of 10 weeks), largely in patients taking atypical antipsychotic drugs, revealed a risk of death in drug-treated patients of between 1.6 to 1.7 times the risk of death in placebo-treated patients. Over the course of a typical 10-week controlled trial, the rate of death in drug-treated patients was about 4.5%, compared to a rate of about 2.6% in the placebo group. Although the causes of death were varied, most of the deaths appeared to be either cardiovascular (e.g., heart failure, sudden death) or infectious (e.g., pneumonia) in nature. Observational studies suggest that, similar to atypical antipsychotic drugs, treatment with conventional antipsychotic drugs may increase mortality. The extent to which the findings of increased mortality in observational studies may be attributed to the antipsychotic drug as opposed to some characteristic(s) of the patients is not clear. SEROQUEL XR is not approved for the treatment of patients with dementia-related psychosis [see Boxed Warning].

5.2 Suicidal Thoughts and Behaviors in Adolescents and Young Adults

Patients with major depressive disorder (MDD), both adult and pediatric, may experience worsening of their depression and/or the emergence of suicidal ideation and behavior (suicidality) or unusual changes in behavior, whether or not they are taking antidepressant medications, and this risk may persist until significant remission occurs. Suicide is a known risk of depression and certain other psychiatric disorders, and these disorders themselves are the strongest predictors of suicide. There has been a long-standing concern, however, that antidepressants may have a role in inducing worsening of depression and the emergence of suicidality in certain patients during the early phases of treatment. Pooled analyses of short-term placebo-controlled trials of antidepressant drugs (SSRIs and others) showed that these drugs increase the risk of suicidal thinking and behavior (suicidality) in children, adolescents, and young adults (ages 18-24) with major depressive disorder (MDD) and other psychiatric disorders. Short-term studies did not show an increase in the risk of suicidality with antidepressants compared to placebo in adults beyond age 24; there was a reduction with antidepressants compared to placebo in adults aged 65 and older.

The pooled analyses of placebo-controlled trials in children and adolescents with MDD, obsessive compulsive disorder (OCD), or other psychiatric disorders included a total of 24 short-term trials of 9 antidepressant drugs in over 4,400 patients. The pooled analyses of placebo-controlled trials in adults with MDD or other psychiatric disorders included a total of 295 short-term trials (median duration of 2 months) of 11 antidepressant drugs in over 77,000 patients. There was considerable variation in risk of suicidality among drugs, but a tendency toward an increase in the younger patients for almost all drugs studied. There were differences in absolute risk of suicidality across the different indications, with the highest incidence in MDD. The risk differences (drug vs. placebo), however, were relatively stable within age strata and across indications. These risk differences (drug-placebo difference in the number of cases of suicidality per 1000 patients treated) are provided in Table 2.

Table 2: Drug-Placebo Difference in Number of Cases of Suicidality per 1000 Patients Treated
Age Range | Drug-Placebo Difference in Number of Cases of Suicidality per 1000 Patients Treated
 | Increases Compared to Placebo
<18 | 14 additional cases
18-24 | 5 additional cases
 | Decreases Compared to Placebo
25-64 | 1 fewer case
≥65 | 6 fewer cases

No suicides occurred in any of the pediatric trials. There were suicides in the adult trials, but the number was not sufficient to reach any conclusion about drug effect on suicide.

It is unknown whether the suicidality risk extends to longer-term use, i.e., beyond several months. However, there is substantial evidence from placebo-controlled maintenance trials in adults with depression that the use of antidepressants can delay the recurrence of depression.

All patients being treated with antidepressants for any indication should be monitored appropriately and observed closely for clinical worsening, suicidality, and unusual changes in behavior, especially during the initial few months of a course of drug therapy, or at times of dose changes, either increases or decreases.

The following symptoms, anxiety, agitation, panic attacks, insomnia, irritability, hostility, aggressiveness, impulsivity, akathisia (psychomotor restlessness), hypomania, and mania, have been reported in adult and pediatric patients being treated with antidepressants for major depressive disorder as well as for other indications, both psychiatric and non-psychiatric. Although a causal link between the emergence of such symptoms and either the worsening of depression and/or the emergence of suicidal impulses has not been established, there is concern that such symptoms may represent precursors to emerging suicidality.

Consideration should be given to changing the therapeutic regimen, including possibly discontinuing the medication, in patients whose depression is persistently worse, or who are experiencing emergent suicidality or symptoms that might be precursors to worsening depression or suicidality, especially if these symptoms are severe, abrupt in onset, or were not part of the patient's presenting symptoms.

Families and caregivers of patients being treated with antidepressants for major depressive disorder or other indications, both psychiatric and non-psychiatric, should be alerted about the need to monitor patients for the emergence of agitation, irritability, unusual changes in behavior, and the other symptoms described above, as well as the emergence of suicidality, and to report such symptoms immediately to healthcare providers. Such monitoring should include daily observation by families and caregivers. Prescriptions for SEROQUEL XR should be written for the smallest quantity of tablets consistent with good patient management, in order to reduce the risk of overdose.

Screening Patients for Bipolar Disorder: A major depressive episode may be the initial presentation of bipolar disorder. It is generally believed (though not established in controlled trials) that treating such an episode with an antidepressant alone may increase the likelihood of precipitation of a mixed/manic episode in patients at risk for bipolar disorder. Whether any of the symptoms described above represent such a conversion is unknown. However, prior to initiating treatment with an antidepressant, including SEROQUEL XR, patients with depressive symptoms should be adequately screened to determine if they are at risk for bipolar disorder; such screening should include a detailed psychiatric history, including a family history of suicide, bipolar disorder, and depression.

5.3 Cerebrovascular Adverse Reactions, Including Stroke, in Elderly Patients with Dementia-Related Psychosis

In placebo-controlled trials with risperidone, aripiprazole, and olanzapine in elderly subjects with dementia, there was a higher incidence of cerebrovascular adverse reactions (cerebrovascular accidents and transient ischemic attacks), including fatalities, compared to placebo-treated subjects. SEROQUEL XR is not approved for the treatment of patients with dementia-related psychosis [see Boxed Warning and Warnings and Precautions (5.1)].

5.4 Neuroleptic Malignant Syndrome (NMS)

A potentially fatal symptom complex sometimes referred to as Neuroleptic Malignant Syndrome (NMS) has been reported in association with administration of antipsychotic drugs, including quetiapine. Rare cases of NMS have been reported with quetiapine. Clinical manifestations of NMS are hyperpyrexia, muscle rigidity, altered mental status, and evidence of autonomic instability (irregular pulse or blood pressure, tachycardia, diaphoresis, and cardiac dysrhythmia). Additional signs may include elevated creatine phosphokinase, myoglobinuria (rhabdomyolysis), and acute renal failure.

The diagnostic evaluation of patients with this syndrome is complicated. In arriving at a diagnosis, it is important to exclude cases where the clinical presentation includes both serious medical illness (e.g., pneumonia, systemic infection, etc.) and untreated or inadequately treated extrapyramidal signs and symptoms (EPS). Other important considerations in the differential diagnosis include central anticholinergic toxicity, heat stroke, drug fever, and primary central nervous system (CNS) pathology.

The management of NMS should include: 1) immediate discontinuation of antipsychotic drugs and other drugs not essential to concurrent therapy; 2) intensive symptomatic treatment and medical monitoring; and 3) treatment of any concomitant serious medical problems for which specific treatments are available. There is no general agreement about specific pharmacological treatment regimens for NMS.

If a patient requires antipsychotic drug treatment after recovery from NMS, the potential reintroduction of drug therapy should be carefully considered. The patient should be carefully monitored since recurrences of NMS have been reported.

5.5 Metabolic Changes

Atypical antipsychotic drugs have been associated with metabolic changes that include hyperglycemia/diabetes mellitus, dyslipidemia, and body weight gain. While all of the drugs in the class have been shown to produce some metabolic changes, each drug has its own specific risk profile. In some patients, a worsening of more than one of the metabolic parameters of weight, blood glucose, and lipids was observed in clinical studies. Changes in these metabolic profiles should be managed as clinically appropriate.

Hyperglycemia and Diabetes Mellitus

Hyperglycemia, in some cases extreme and associated with ketoacidosis or hyperosmolar coma or death, has been reported in patients treated with atypical antipsychotics, including quetiapine. Assessment of the relationship between atypical antipsychotic use and glucose abnormalities is complicated by the possibility of an increased background risk of diabetes mellitus in patients with schizophrenia and the increasing incidence of diabetes mellitus in the general population. Given these confounders, the relationship between atypical antipsychotic use and hyperglycemia-related adverse reactions is not completely understood. However, epidemiological studies suggest an increased risk of hyperglycemia-related adverse reactions in patients treated with the atypical antipsychotics. Precise risk estimates for hyperglycemia-related adverse reactions in patients treated with atypical antipsychotics are not available.

Patients with an established diagnosis of diabetes mellitus who are started on atypical antipsychotics should be monitored regularly for worsening of glucose control. Patients with risk factors for diabetes mellitus (e.g., obesity, family history of diabetes) who are starting treatment with atypical antipsychotics should undergo fasting blood glucose testing at the beginning of treatment and periodically during treatment. Any patient treated with atypical antipsychotics should be monitored for symptoms of hyperglycemia including polydipsia, polyuria, polyphagia, and weakness. Patients who develop symptoms of hyperglycemia during treatment with atypical antipsychotics should undergo fasting blood glucose testing. In some cases, hyperglycemia has resolved when the atypical antipsychotic was discontinued; however, some patients required continuation of anti-diabetic treatment despite discontinuation of the suspect drug.

Adults:

Table 3: Fasting Glucose-Proportion of Patients Shifting to ≥126 mg/dL in Short-Term (≤12 weeks) Placebo-Controlled Studies [Includes SEROQUEL and SEROQUEL XR data.]
Laboratory; Analyte | Category Change; (At Least Once) from Baseline | Treatment Arm | N | Patients; n (%)
Fasting Glucose | Normal to High; (<100 mg/dL to ≥126 mg/dL) | Quetiapine | 2907 | 71 (2.4%)
Fasting Glucose | Normal to High; (<100 mg/dL to ≥126 mg/dL) | Placebo | 1346 | 19 (1.4%)
Fasting Glucose | Borderline to High(≥100 mg/dL and <126 mg/dL to ≥126 mg/dL) | Quetiapine | 572 | 67 (11.7%)
Fasting Glucose | Borderline to High(≥100 mg/dL and <126 mg/dL to ≥126 mg/dL) | Placebo | 279 | 33 (11.8%)

In a 24-week trial (active-controlled, 115 patients treated with SEROQUEL) designed to evaluate glycemic status with oral glucose tolerance testing of all patients, at week 24 the incidence of post-glucose challenge glucose level ≥200 mg/dL was 1.7% and the incidence of a fasting blood glucose level ≥126 mg/dL was 2.6%. The mean change in fasting glucose from baseline was 3.2 mg/dL and mean change in 2-hour glucose from baseline was -1.8 mg/dL for quetiapine.

In 2 long-term placebo-controlled randomized withdrawal clinical trials for bipolar I disorder maintenance, mean exposure of 213 days for SEROQUEL (646 patients) and 152 days for placebo (680 patients), the mean change in glucose from baseline was +5.0 mg/dL for quetiapine and -0.05 mg/dL for placebo. The exposure-adjusted rate of any increased blood glucose level (≥126 mg/dL) for patients more than 8 hours since a meal (however, some patients may not have been precluded from calorie intake from fluids during fasting period) was 18.0 per 100 patient years for SEROQUEL (10.7% of patients; n=556) and 9.5 for placebo per 100 patient years (4.6% of patients; n=581).

Table 4 shows the percentage of patients with shifts in blood glucose to ≥126 mg/dL from normal baseline in MDD adjunct therapy trials by dose.

Table 4: Percentage of Patients with Shifts from Normal Baseline in Blood Glucose to ≥126 mg/dL (assumed fasting) in MDD Adjunct Therapy Trials by Dose
Laboratory Analyte | Treatment Arm | N | Patientsn (%)
Blood Glucose ≥126 mg/dL | SEROQUEL XR 150 mg | 280 | 19 (7%)
Blood Glucose ≥126 mg/dL | SEROQUEL XR 300 mg | 269 | 32 (12%)
Blood Glucose ≥126 mg/dL | Placebo | 277 | 17 (6%)

Children and Adolescents:

Safety and effectiveness of SEROQUEL XR is supported from studies of SEROQUEL in children and adolescent patients 10 to 17 years of age [see Clinical Studies (14.2)]. In a placebo-controlled SEROQUEL XR monotherapy study (8 weeks duration) of children and adolescent patients (10-17 years of age) with bipolar depression, in which efficacy was not established, the mean change in fasting glucose levels for SEROQUEL XR (n=60) compared to placebo (n=62) was 1.8 mg/dL versus 1.6 mg/dL. In this study, there were no patients in the SEROQUEL XR or placebo-treated groups with a baseline normal fasting glucose level (<100 mg/dL) that had an increase in blood glucose level ≥126 mg/dL. There was one patient in the SEROQUEL XR group with a baseline borderline fasting glucose level (≥100 mg/dL and <126 mg/dL) who had an increase in blood glucose level of >126 mg/dL compared to zero patients in the placebo group.

In a placebo-controlled SEROQUEL monotherapy study of adolescent patients (13-17 years of age) with schizophrenia (6 weeks duration), the mean change in fasting glucose levels for SEROQUEL (n=138) compared to placebo (n=67) was -0.75 mg/dL versus -1.70 mg/dL. In a placebo-controlled SEROQUEL monotherapy study of children and adolescent patients (10-17 years of age) with bipolar mania (3 weeks duration), the mean change in fasting glucose level for SEROQUEL (n=170) compared to placebo (n=81) was 3.62 mg/dL versus -1.17 mg/dL. No patient in either study with a baseline normal fasting glucose level (<100 mg/dL) or a baseline borderline fasting glucose level (≥100 mg/dL and <126 mg/dL) had a blood glucose level of ≥126 mg/dL.

Dyslipidemia

Adults:

Table 5 shows the percentage of patients with changes in cholesterol and triglycerides from baseline by indication in clinical trials with SEROQUEL XR.

Table 5: Percentage of Adult Patients with Shifts in Total Cholesterol, Triglycerides, LDL-Cholesterol and HDL-Cholesterol from Baseline to Clinically Significant Levels by Indication
Laboratory Analyte | Indication | Treatment Arm | N | Patientsn (%)
Total Cholesterol; ≥240 mg/dL | Schizophrenia [6 weeks duration] | SEROQUEL XR | 718 | 67 (9%)
Total Cholesterol; ≥240 mg/dL | Schizophrenia [6 weeks duration] | Placebo | 232 | 21 (9%)
Total Cholesterol; ≥240 mg/dL | Bipolar Depression [8 weeks duration] | SEROQUEL XR | 85 | 6 (7%)
Total Cholesterol; ≥240 mg/dL | Bipolar Depression [8 weeks duration] | Placebo | 106 | 3 (3%)
Total Cholesterol; ≥240 mg/dL | Bipolar Mania [3 weeks duration] | SEROQUEL XR | 128 | 9 (7%)
Total Cholesterol; ≥240 mg/dL | Bipolar Mania [3 weeks duration] | Placebo | 134 | 5 (4%)
Total Cholesterol; ≥240 mg/dL | Major Depressive Disorder (Adjunct Therapy) | SEROQUEL XR | 420 | 67 (16%)
Total Cholesterol; ≥240 mg/dL | Major Depressive Disorder (Adjunct Therapy) | Placebo | 213 | 15 (7%)
Triglycerides; ≥200 mg/dL | Schizophrenia | SEROQUEL XR | 659 | 118 (18%)
Triglycerides; ≥200 mg/dL | Schizophrenia | Placebo | 214 | 11 (5%)
Triglycerides; ≥200 mg/dL | Bipolar Depression | SEROQUEL XR | 84 | 7 (8%)
Triglycerides; ≥200 mg/dL | Bipolar Depression | Placebo | 93 | 7 (8%)
Triglycerides; ≥200 mg/dL | Bipolar Mania | SEROQUEL XR | 102 | 15 (15%)
Triglycerides; ≥200 mg/dL | Bipolar Mania | Placebo | 125 | 8 (6%)
Triglycerides; ≥200 mg/dL | Major Depressive Disorder (Adjunct Therapy) | SEROQUEL XR | 458 | 75 (16%)
Triglycerides; ≥200 mg/dL | Major Depressive Disorder (Adjunct Therapy) | Placebo | 223 | 18 (8%)
LDL-Cholesterol; ≥160 mg/dL | Schizophrenia | SEROQUEL XR | 691 | 47 (7%)
LDL-Cholesterol; ≥160 mg/dL | Schizophrenia | Placebo | 227 | 17 (8%)
LDL-Cholesterol; ≥160 mg/dL | Bipolar Depression | SEROQUEL XR | 86 | 3 (4%)
LDL-Cholesterol; ≥160 mg/dL | Bipolar Depression | Placebo | 104 | 2 (2%)
LDL-Cholesterol; ≥160 mg/dL | Bipolar Mania | SEROQUEL XR | 125 | 5 (4%)
LDL-Cholesterol; ≥160 mg/dL | Bipolar Mania | Placebo | 135 | 2 (2%)
LDL-Cholesterol; ≥160 mg/dL | Major Depressive Disorder (Adjunct Therapy) | SEROQUEL XR | 457 | 51 (11%)
LDL-Cholesterol; ≥160 mg/dL | Major Depressive Disorder (Adjunct Therapy) | Placebo | 219 | 21 (10%)
HDL-Cholesterol; ≤40 mg/dL | Schizophrenia | SEROQUEL XR | 600 | 87 (15%)
HDL-Cholesterol; ≤40 mg/dL | Schizophrenia | Placebo | 195 | 23 (12%)
HDL-Cholesterol; ≤40 mg/dL | Bipolar Depression | SEROQUEL XR | 78 | 7 (9%)
HDL-Cholesterol; ≤40 mg/dL | Bipolar Depression | Placebo | 83 | 6 (7%)
HDL-Cholesterol; ≤40 mg/dL | Bipolar Mania | SEROQUEL XR | 100 | 19 (19%)
HDL-Cholesterol; ≤40 mg/dL | Bipolar Mania | Placebo | 115 | 15 (13%)
HDL-Cholesterol; ≤40 mg/dL | Major Depressive Disorder (Adjunct Therapy) | SEROQUEL XR | 470 | 34 (7%)
HDL-Cholesterol; ≤40 mg/dL | Major Depressive Disorder (Adjunct Therapy) | Placebo | 230 | 19 (8%)

In SEROQUEL clinical trials for schizophrenia, the percentage of patients with shifts in cholesterol and triglycerides from baseline to clinically significant levels were 18% (placebo: 7%) and 22% (placebo: 16%). HDL-cholesterol and LDL-cholesterol parameters were not measured in these studies. In SEROQUEL clinical trials for bipolar depression, the following percentage of patients had shifts from baseline to clinically significant levels for the four lipid parameters measured: total cholesterol 9% (placebo: 6%); triglycerides 14% (placebo: 9%); LDL-cholesterol 6% (placebo: 5%) and HDL-cholesterol 14% (placebo: 14%). Lipid parameters were not measured in the bipolar mania studies.

Table 6 shows the percentage of patients in MDD adjunctive therapy trials with clinically significant shifts in total-cholesterol, triglycerides, LDL-cholesterol and HDL-cholesterol from baseline by dose.

Table 6: Percentage of Patients with Shifts in Total Cholesterol, Triglycerides, LDL-Cholesterol, and HDL-Cholesterol from Baseline to Clinically Significant Levels in MDD Adjunctive Therapy Trials by Dose
Laboratory; Analyte | Treatment Arm [6 weeks duration] | N | Patients; n (%)
Cholesterol; ≥240 mg/dL | SEROQUEL XR 150 mg | 223 | 41 (18%)
Cholesterol; ≥240 mg/dL | SEROQUEL XR 300 mg | 197 | 26 (13%)
Cholesterol; ≥240 mg/dL | Placebo | 213 | 15 (7%)
Triglycerides; ≥200 mg/dL | SEROQUEL XR 150 mg | 232 | 36 (16%)
Triglycerides; ≥200 mg/dL | SEROQUEL XR 300 mg | 226 | 39 (17%)
Triglycerides; ≥200 mg/dL | Placebo | 223 | 18 (8%)
LDL-Cholesterol; ≥160 mg/dL | SEROQUEL XR 150 mg | 242 | 29 (12%)
LDL-Cholesterol; ≥160 mg/dL | SEROQUEL XR 300 mg | 215 | 22 (10%)
LDL-Cholesterol; ≥160 mg/dL | Placebo | 219 | 21 (10%)
HDL-Cholesterol; ≤40 mg/dL | SEROQUEL XR 150 mg | 238 | 14 (6%)
HDL-Cholesterol; ≤40 mg/dL | SEROQUEL XR 300 mg | 232 | 20 (9%)
HDL-Cholesterol; ≤40 mg/dL | Placebo | 230 | 19 (8%)

Children and Adolescents:

Safety and effectiveness of SEROQUEL XR is supported by studies of SEROQUEL in children and adolescent patients 10 to 17 years of age [see Clinical Studies (14.1 and 14.2)].

In a placebo-controlled SEROQUEL XR monotherapy study (8 weeks duration) of children and adolescent patients (10-17 years of age) with bipolar depression, in which efficacy was not established, the percentage of children and adolescents with shifts in total cholesterol (≥200 mg/dL), triglycerides (≥150 mg/dL), LDL-cholesterol (≥130 mg/dL), and HDL-cholesterol (≤40 mg/dL) from baseline to clinically significant levels were: total cholesterol 8% (7/83) for SEROQUEL XR vs. 6% (5/84) for placebo; triglycerides 28% (22/80) for SEROQUEL XR vs. 9% (7/82) for placebo; LDL-cholesterol 2% (2/86) for SEROQUEL XR vs. 4% (3/85) for placebo and HDL-cholesterol 20% (13/65) for SEROQUEL XR vs. 15% (11/74) for placebo.

Table 7 shows the percentage of children and adolescents with shifts in total cholesterol, triglycerides, LDL-cholesterol, and HDL-cholesterol from baseline to clinically significant levels by indication in clinical trials with SEROQUEL in adolescents (13-17 years) with schizophrenia and in children and adolescents (10-17 years) with bipolar mania.

Table 7: Percentage of Children and Adolescents with Shifts in Total Cholesterol, Triglycerides, LDL-Cholesterol, and HDL-Cholesterol from Baseline to Clinically Significant Levels by Indication
Laboratory Analyte | Indication | Treatment Arm | N | Patientsn (%)
Total Cholesterol ≥200 mg/dL | Schizophrenia [13-17 years, 6 weeks duration] | SEROQUEL | 107 | 13 (12%)
Total Cholesterol ≥200 mg/dL | Schizophrenia [13-17 years, 6 weeks duration] | Placebo | 56 | 1 (2%)
Total Cholesterol ≥200 mg/dL | Bipolar Mania [10-17 years, 3 weeks duration] | SEROQUEL | 159 | 16 (10%)
Total Cholesterol ≥200 mg/dL | Bipolar Mania [10-17 years, 3 weeks duration] | Placebo | 66 | 2 (3%)
Triglycerides ≥150 mg/dL | Schizophrenia | SEROQUEL | 103 | 17 (17%)
Triglycerides ≥150 mg/dL | Schizophrenia | Placebo | 51 | 4 (8%)
Triglycerides ≥150 mg/dL | Bipolar Mania | SEROQUEL | 149 | 32 (22%)
Triglycerides ≥150 mg/dL | Bipolar Mania | Placebo | 60 | 8 (13%)
LDL-Cholesterol ≥130 mg/dL | Schizophrenia | SEROQUEL | 112 | 4 (4%)
LDL-Cholesterol ≥130 mg/dL | Schizophrenia | Placebo | 60 | 1 (2%)
LDL-Cholesterol ≥130 mg/dL | Bipolar Mania | SEROQUEL | 169 | 13 (8%)
LDL-Cholesterol ≥130 mg/dL | Bipolar Mania | Placebo | 74 | 4 (5%)
HDL-Cholesterol ≤40 mg/dL | Schizophrenia | SEROQUEL | 104 | 16 (15%)
HDL-Cholesterol ≤40 mg/dL | Schizophrenia | Placebo | 54 | 10 (19%)
HDL-Cholesterol ≤40 mg/dL | Bipolar Mania | SEROQUEL | 154 | 16 (10%)
HDL-Cholesterol ≤40 mg/dL | Bipolar Mania | Placebo | 61 | 4 (7%)

Weight Gain

Increases in weight have been observed in clinical trials. Patients receiving quetiapine should receive regular monitoring of weight.

Adults: Table 8 shows the percentage of adult patients with weight gain of ≥7% of body weight by indication.

Table 8: Percentage of Patients with Weight Gain ≥7% of Body Weight (Adults) by Indication
Vital sign | Indication | Treatment Arm | N | Patientsn (%)
Weight Gain ≥7% of Body Weight | Schizophrenia [6 weeks duration] | SEROQUEL XR | 907 | 90 (10%)
Weight Gain ≥7% of Body Weight | Schizophrenia [6 weeks duration] | Placebo | 299 | 16 (5%)
Weight Gain ≥7% of Body Weight | Bipolar Mania [3 weeks duration] | SEROQUEL XR | 138 | 7 (5%)
Weight Gain ≥7% of Body Weight | Bipolar Mania [3 weeks duration] | Placebo | 150 | 0 (0%)
Weight Gain ≥7% of Body Weight | Bipolar Depression [8 weeks duration] | SEROQUEL XR | 110 | 9 (8%)
Weight Gain ≥7% of Body Weight | Bipolar Depression [8 weeks duration] | Placebo | 125 | 1 (1%)
Weight Gain ≥7% of Body Weight | Major Depressive Disorder (Adjunctive Therapy) | SEROQUEL XR | 616 | 32 (5%)
Weight Gain ≥7% of Body Weight | Major Depressive Disorder (Adjunctive Therapy) | Placebo | 302 | 5 (2%)

In schizophrenia trials, the proportions of patients meeting a weight gain criterion of ≥7% of body weight were compared in a pool of four 3- to 6-week placebo-controlled clinical trials, revealing a statistically significant greater incidence of weight gain for SEROQUEL (23%) compared to placebo (6%).

Table 9 shows the percentage of adult patients with weight gain of ≥7% of body weight for MDD by dose.

Table 9: Percentage of Patients with Weight Gain ≥7% of Body Weight in MDD Adjunctive Therapy Trials by Dose (Adults)
Vital sign | Treatment Arm | N | Patientsn (%)
Weight Gain ≥7% of Body Weight in MDD Adjunctive Therapy | SEROQUEL XR150 mg | 309 | 10 (3%)
Weight Gain ≥7% of Body Weight in MDD Adjunctive Therapy | SEROQUEL XR300 mg | 307 | 22 (7%)
Weight Gain ≥7% of Body Weight in MDD Adjunctive Therapy | Placebo | 302 | 5 (2%)

Children and Adolescents: Safety and effectiveness of SEROQUEL XR is supported by studies of SEROQUEL in children and adolescent patients 10 to 17 years of age [see Clinical Studies (14.1 and 14.2)]. In a clinical trial for SEROQUEL XR in children and adolescents (10-17 years of age) with bipolar depression, in which efficacy was not established, the percentage of patients with weight gain ≥7% of body weight at any time was 15% (14/92) for SEROQUEL XR vs. 10% (10/100) for placebo. The mean change in body weight was 1.4 kg in the SEROQUEL XR group vs. 0.6 kg in the placebo group.

Weight gain was greater in patients 10-12 years of age compared to patients 13-17 years of age. The percentage of patients 10-12 years of age with weight gain ≥7% at any time was 28% (7/25) for SEROQUEL XR vs. 0% (0/28) for placebo. The percentage of patients 13-17 years of age with weight gain ≥7% at any time was 10.4% (7/67) for SEROQUEL XR vs. 13.9% (10/72) for placebo.

Table 10 shows the percentage of children and adolescents with weight gain ≥7% of body weight in clinical trials with SEROQUEL in adolescents (13-17 years) with schizophrenia and in children and adolescents (10-17 years) with bipolar mania.

Table 10: Percentage of Patients with Weight Gain ≥7% of Body Weight (Children and Adolescents)
Vital sign | Indication | Treatment Arm | N | Patientsn (%)
Weight Gain ≥7% of Body Weight | Schizophrenia [6 weeks duration] | SEROQUEL | 111 | 23 (21%)
Weight Gain ≥7% of Body Weight | Schizophrenia [6 weeks duration] | Placebo | 44 | 3 (7%)
Weight Gain ≥7% of Body Weight | Bipolar Mania [3 weeks duration] | SEROQUEL | 157 | 18 (12%)
Weight Gain ≥7% of Body Weight | Bipolar Mania [3 weeks duration] | Placebo | 68 | 0 (0%)

The mean change in body weight in the schizophrenia trial was 2.0 kg in the SEROQUEL group and -0.4 kg in the placebo group and in the bipolar mania trial it was 1.7 kg in the SEROQUEL group and 0.4 kg in the placebo group.

In an open-label study that enrolled patients from the above two pediatric trials, 63% of patients (241/380) completed 26 weeks of therapy with SEROQUEL. After 26 weeks of treatment, the mean increase in body weight was 4.4 kg. Forty-five percent of the patients gained ≥7% of their body weight, not adjusted for normal growth. In order to adjust for normal growth over 26 weeks, an increase of at least 0.5 standard deviation from baseline in BMI was used as a measure of a clinically significant change; 18.3% of patients on SEROQUEL met this criterion after 26 weeks of treatment.

When treating pediatric patients with SEROQUEL for any indication, weight gain should be assessed against that expected for normal growth.

5.6 Tardive Dyskinesia

A syndrome of potentially irreversible, involuntary, dyskinetic movements may develop in patients treated with antipsychotic drugs including quetiapine. Although the prevalence of the syndrome appears to be highest among the elderly, especially elderly women, it is impossible to rely upon prevalence estimates to predict, at the inception of antipsychotic treatment, which patients are likely to develop the syndrome. Whether antipsychotic drug products differ in their potential to cause tardive dyskinesia is unknown.

The risk of developing tardive dyskinesia and the likelihood that it will become irreversible are believed to increase as the duration of treatment and the total cumulative dose of antipsychotic drugs administered to the patient increase. However, the syndrome can develop, although much less commonly, after relatively brief treatment periods at low doses or may even arise after discontinuation of treatment.

Tardive dyskinesia may remit, partially or completely, if antipsychotic treatment is withdrawn. Antipsychotic treatment, itself, however, may suppress (or partially suppress) the signs and symptoms of the syndrome and thereby may possibly mask the underlying process. The effect that symptomatic suppression has upon the long-term course of the syndrome is unknown.

Given these considerations, SEROQUEL XR should be prescribed in a manner that is most likely to minimize the occurrence of tardive dyskinesia. Chronic antipsychotic treatment should generally be reserved for patients who appear to suffer from a chronic illness that (1) is known to respond to antipsychotic drugs, and (2) for whom alternative, equally effective, but potentially less harmful treatments are not available or appropriate. In patients who do require chronic treatment, the smallest dose and the shortest duration of treatment producing a satisfactory clinical response should be sought. The need for continued treatment should be reassessed periodically.

If signs and symptoms of tardive dyskinesia appear in a patient on SEROQUEL XR, drug discontinuation should be considered. However, some patients may require treatment with quetiapine despite the presence of the syndrome.

5.7 Hypotension

Quetiapine may induce orthostatic hypotension associated with dizziness, tachycardia and, in some patients, syncope, especially during the initial dose-titration period, probably reflecting its ά1-adrenergic antagonist properties. Syncope was reported in 0.3% (5/1866) of the patients treated with SEROQUEL XR across all indications, compared with 0.2% (2/928) on placebo. Syncope was reported in 1% (28/3265) of the patients treated with SEROQUEL, compared with 0.2% (2/954) on placebo. Orthostatic hypotension, dizziness, and syncope may lead to falls.

Quetiapine should be used with particular caution in patients with known cardiovascular disease (history of myocardial infarction or ischemic heart disease, heart failure, or conduction abnormalities), cerebrovascular disease, or conditions which would predispose patients to hypotension (dehydration, hypovolemia, and treatment with antihypertensive medications). If hypotension occurs during titration to the target dose, a return to the previous dose in the titration schedule is appropriate.

5.8 Falls

Atypical antipsychotic drugs, including SEROQUEL XR, may cause somnolence, postural hypotension, motor, and sensory instability, which may lead to falls and, consequently, fractures or other injuries. For patients with diseases, conditions, or medications that could exacerbate these effects, complete fall risk assessments when initiating antipsychotic treatment and recurrently for patients on long-term antipsychotic therapy.

5.9 Increases in Blood Pressure (Children and Adolescents)

Safety and effectiveness of SEROQUEL XR is supported by studies of SEROQUEL in children and adolescent patients 10 - 17 years of age [see Clinical Studies (14.1 and 14.2)].

In a placebo-controlled SEROQUEL XR clinical trial (8 weeks duration) in children and adolescents (10-17 years of age) with bipolar depression, in which efficacy was not established, the incidence of increases at any time in systolic blood pressure (≥20 mmHg) was 6.5% (6/92) for SEROQUEL XR and 6.0% (6/100) for placebo; the incidence of increases at any time in diastolic blood pressure (≥10 mmHg) was 46.7% (43/92) for SEROQUEL XR and 36.0% (36/100) for placebo.

In placebo-controlled trials in children and adolescents with schizophrenia (13-17 years old, 6-week duration) or bipolar mania (10-17 years old, 3-week duration), the incidence of increases at any time in systolic blood pressure (≥20 mmHg) was 15.2% (51/335) for SEROQUEL and 5.5% (9/163) for placebo; the incidence of increases at any time in diastolic blood pressure (≥10 mmHg) was 40.6% (136/335) for SEROQUEL and 24.5% (40/163) for placebo. In the 26-week open-label clinical trial, one child with a reported history of hypertension experienced a hypertensive crisis. Blood pressure in children and adolescents should be measured at the beginning of, and periodically during treatment.

5.10 Leukopenia, Neutropenia, and Agranulocytosis

In clinical trials and postmarketing experience, events of leukopenia/neutropenia have been reported temporally related to atypical antipsychotic agents, including quetiapine. Agranulocytosis has also been reported.

Agranulocytosis has been reported with quetiapine, including fatal cases and cases in patients without pre-existing risk factors. Neutropenia should be considered in patients presenting with infection, particularly in the absence of obvious predisposing factor(s), or in patients with unexplained fever, and should be managed as clinically appropriate.

Possible risk factors for leukopenia/neutropenia include pre-existing low white cell count (WBC) and history of drug induced leukopenia/neutropenia. Patients with a pre-existing low WBC or a history of drug induced leukopenia/neutropenia should have their complete blood count (CBC) monitored frequently during the first few months of therapy and should discontinue SEROQUEL XR at the first sign of a decline in WBC in absence of other causative factors.

Patients with neutropenia should be carefully monitored for fever or other symptoms or signs of infection and treated promptly if such symptoms or signs occur. Patients with severe neutropenia (absolute neutrophil count <1000/mm3) should discontinue SEROQUEL XR and have their WBC followed until recovery.

5.11 Cataracts

The development of cataracts was observed in association with quetiapine treatment in chronic dog studies [see Nonclinical Toxicology (13.2)]. Lens changes have also been observed in adults, children, and adolescents during long-term quetiapine treatment but a causal relationship to quetiapine use has not been established. Nevertheless, the possibility of lenticular changes cannot be excluded at this time. Therefore, examination of the lens by methods adequate to detect cataract formation, such as slit lamp exam or other appropriately sensitive methods, is recommended at initiation of treatment or shortly thereafter, and at 6-month intervals during chronic treatment.

5.12 QT Prolongation

In clinical trials quetiapine was not associated with a persistent increase in QT intervals. However, the QT effect was not systematically evaluated in a thorough QT study. In post marketing experience there were cases reported of QT prolongation in patients who overdosed on quetiapine [see Overdosage (10.1)], in patients with concomitant illness, and in patients taking medicines known to cause electrolyte imbalance or increase QT interval.

The use of quetiapine should be avoided in combination with other drugs that are known to prolong QTc including Class 1A antiarrythmics (e.g., quinidine, procainamide) or Class III antiarrythmics (e.g., amiodarone, sotalol), antipsychotic medications (e.g., ziprasidone, chlorpromazine, thioridazine), antibiotics (e.g., gatifloxacin, moxifloxacin), or any other class of medications known to prolong the QTc interval (e.g., pentamidine, levomethadyl acetate, methadone).

Quetiapine should also be avoided in circumstances that may increase the risk of occurrence of torsade de pointes and/or sudden death including (1) a history of cardiac arrhythmias such as bradycardia; (2) hypokalemia or hypomagnesemia; (3) concomitant use of other drugs that prolong the QTc interval; and (4) presence of congenital prolongation of the QT interval.

Caution should also be exercised when quetiapine is prescribed in patients with increased risk of QT prolongation (e.g., cardiovascular disease, family history of QT prolongation, the elderly, congestive heart failure, and heart hypertrophy).

5.13 Seizures

During short-term clinical trials with SEROQUEL XR, seizures occurred in 0.05% (1/1866) of patients treated with SEROQUEL XR across all indications compared to 0.3% (3/928) on placebo. During clinical trials with SEROQUEL, seizures occurred in 0.5% (20/3490) of patients treated with SEROQUEL compared to 0.2% (2/954) on placebo. As with other antipsychotics, quetiapine should be used cautiously in patients with a history of seizures or with conditions that potentially lower the seizure threshold, e.g., Alzheimer’s dementia. Conditions that lower the seizure threshold may be more prevalent in a population of 65 years or older.

5.14 Hypothyroidism

Adults: Clinical trials with quetiapine demonstrated dose-related decreases in thyroid hormone levels. The reduction in total and free thyroxine (T4) of approximately 20% at the higher end of the therapeutic dose range was maximal in the first six weeks of treatment and maintained without adaptation or progression during more chronic therapy. In nearly all cases, cessation of quetiapine treatment was associated with a reversal of the effects on total and free T4, irrespective of the duration of treatment. The mechanism by which quetiapine effects the thyroid axis is unclear. If there is an effect on the hypothalamic-pituitary axis, measurement of TSH alone may not accurately reflect a patient’s thyroid status. Therefore, both TSH and free T4, in addition to clinical assessment, should be measured at baseline and at follow-up.

In SEROQUEL XR clinical trials across all indications 1.8% (24/1336) of patients on SEROQUEL XR versus 0.6% (3/530) on placebo experienced decreased free thyroxine (<0.8 LLN) and 1.6% (21/1346) on SEROQUEL XR vs. 3.4% (18/534) on placebo experienced increased thyroid stimulating hormone (TSH). About 0.7% (26/3489) of SEROQUEL patients did experience TSH increases in monotherapy studies. Some patients with TSH increases needed replacement thyroid treatment.

In all quetiapine trials, the incidence of shifts in thyroid hormones and TSH were1: decrease in free T4 (<0.8 LLN), 2.0% (357/17513); decrease in total T4 (<0.8 LLN), 4.0% (75/1861); decrease in free T3 (<0.8 LLN), 0.4% (53/13766); decrease in total T3 (<0.8 LLN), 2.0% (26/1312), and increase in TSH (>5 mIU/L), 4.9% (956/19412). In eight patients, where TBG was measured, levels of TBG were unchanged.

_______________________

^1Based on shifts from normal baseline to potentially clinically important value at anytime post-baseline. Shifts in total T4, free T4, total T3 and free T3 are defined as <0.8 x LLN (pmol/L) and shift in TSH is >5 mIU/L at any time.

Table 11 shows the incidence of these shifts in short term placebo-controlled clinical trials.

Table 11: Incidence of Shifts in Thyroid Hormone Levels and TSH in Short-term Placebo-controlled Clinical Trials [Based on shifts from normal baseline to potentially clinically important value at anytime post-baseline. Shifts in total T4, free T4, total T3, and free T3 are defined as <0.8 x LLN (pmol/L) and shift in TSH is >5 mIU/L at any time.] [Includes SEROQUEL and SEROQUEL XR data.]
Total T4 |  | Free T4 |  | Total T3 |  | Free T3 |  | TSH
Quetiapine | Placebo | Quetiapine | Placebo | Quetiapine | Placebo | Quetiapine | Placebo | Quetiapine | Placebo
3.4%; (37/1097) | 0.6%; (4/651) | 0.7%; (52/7218) | 0.1%; (4/3668) | 0.5%; (2/369) | 0.0%; (0/113) | 0.2%; (11/5673) | 0.0%; (1/2679) | 3.2%; (240/7587) | 2.7%; (105/3912)

In short-term placebo-controlled monotherapy trials, the incidence of reciprocal shifts in T3 and TSH was 0.0 % for both quetiapine (1/4800) and placebo (0/2190) and for T4 and TSH the shifts were 0.1% (7/6154) for quetiapine versus 0.0 % (1/3007) for placebo.

Children and Adolescents: Safety and effectiveness of SEROQUEL XR is supported by studies of SEROQUEL in children and adolescent patients 10 - 17 years of age [see Clinical Studies (14.1 and 14.2)].

In acute placebo-controlled trials in children and adolescent patients with schizophrenia (6-week duration) or bipolar mania (3-week duration), the incidence of shifts at any time for SEROQUEL treated patients and placebo-treated patients for elevated TSH was 2.9% (8/280) vs. 0.7% (1/138), respectively, and for decreased total thyroxine was 2.8% (8/289) vs. 0% (0/145), respectively. Of the SEROQUEL treated patients with elevated TSH levels, 1 had simultaneous low free T4 level at end of treatment.

5.15 Hyperprolactinemia

Adults: During clinical trials with quetiapine across all indications, the incidence of shifts in prolactin levels to a clinically significant value occurred in 3.6% (158/4416) of patients treated with quetiapine compared to 2.6% (51/1968) on placebo.

Children and Adolescents: Safety and effectiveness of SEROQUEL XR is supported by studies of SEROQUEL in children and adolescent patients 10 - 17 years of age [see Clinical Studies (14.1 and 14.2)]. In acute placebo-controlled trials in children and adolescent patients with bipolar mania (3-week duration) or schizophrenia (6-week duration), the incidence of shifts in prolactin levels to a value (>20 µg/L males; >26 µg/L females at any time) was 13.4% (18/134) for SEROQUEL compared to 4% (3/75) for placebo in males and 8.7% (9/104) for SEROQUEL compared to 0% (0/39) for placebo in females.

Like other drugs that antagonize dopamine D2 receptors, SEROQUEL XR elevates prolactin levels in some patients and the elevation may persist during chronic administration. Hyperprolactinemia, regardless of etiology, may suppress hypothalamic GnRH, resulting in reduced pituitary gonadotrophin secretion. This, in turn, may inhibit reproductive function by impairing gonadal steroidogenesis in both female and male patients. Galactorrhea, amenorrhea, gynecomastia, and impotence have been reported in patients receiving prolactin-elevating compounds. Long-standing hyperprolactinemia when associated with hypogonadism may lead to decreased bone density in both female and male subjects.

Tissue culture experiments indicate that approximately one-third of human breast cancers are prolactin dependent in vitro, a factor of potential importance if the prescription of these drugs is considered in a patient with previously detected breast cancer. As is common with compounds which increase prolactin release, mammary gland, and pancreatic islet cell neoplasia (mammary adenocarcinomas, pituitary, and pancreatic adenomas) was observed in carcinogenicity studies conducted in mice and rats [see Nonclinical Toxicology (13.1)]. Published epidemiologic studies have shown inconsistent results when exploring the potential association between hyperprolactinemia and breast cancer.

5.16 Potential for Cognitive and Motor Impairment

Somnolence was a commonly reported adverse reaction reported in patients treated with quetiapine especially during the 3-day period of initial dose titration. In schizophrenia trials, somnolence was reported in 24.7% (235/951) of patients on SEROQUEL XR compared to 10.3% (33/319) of placebo patients. In a bipolar depression clinical trial, somnolence was reported in 51.8% (71/137) of patients on SEROQUEL XR compared to 12.9% (18/140) of placebo patients. In a clinical trial for bipolar mania, somnolence was reported in 50.3% (76/151) of patients on SEROQUEL XR compared to 11.9% (19/160) of placebo patients. Since quetiapine has the potential to impair judgment, thinking, or motor skills, patients should be cautioned about performing activities requiring mental alertness, such as operating a motor vehicle (including automobiles) or operating hazardous machinery until they are reasonably certain that quetiapine therapy does not affect them adversely. Somnolence may lead to falls.

In short-term adjunctive therapy trials for MDD, somnolence was reported in 40% (252/627) of patients on SEROQUEL XR respectively compared to 9% (27/309) of placebo patients. Somnolence was dose-related in these trials (37% (117/315) and 43% (135/312) for the 150 mg and 300 mg groups, respectively).

5.17 Body Temperature Regulation

Disruption of the body's ability to reduce core body temperature has been attributed to antipsychotic agents. Appropriate care is advised when prescribing SEROQUEL XR for patients who will be experiencing conditions which may contribute to an elevation in core body temperature, e.g., exercising strenuously, exposure to extreme heat, receiving concomitant medication with anticholinergic activity, or being subject to dehydration.

5.18 Dysphagia

Esophageal dysmotility and aspiration have been associated with antipsychotic drug use. Aspiration pneumonia is a common cause of morbidity and mortality in elderly patients, in particular those with advanced Alzheimer's dementia. SEROQUEL XR and other antipsychotic drugs should be used cautiously in patients at risk for aspiration pneumonia.

5.19 Discontinuation Syndrome

Acute withdrawal symptoms, such as insomnia, nausea, and vomiting have been described after abrupt cessation of atypical antipsychotic drugs, including quetiapine. In short-term placebo-controlled, monotherapy clinical trials with SEROQUEL XR that included a discontinuation phase which evaluated discontinuation symptoms, the aggregated incidence of patients experiencing one or more discontinuation symptoms after abrupt cessation was 12.1% (241/1993) for SEROQUEL XR and 6.7% (71/1065) for placebo. The incidence of the individual adverse reactions (i.e., insomnia, nausea, headache, diarrhea, vomiting, dizziness, and irritability) did not exceed 5.3% in any treatment group and usually resolved after 1-week post-discontinuation. Gradual dose reduction is advised [see Use in Specific Populations (8.1)].

5.20 Anticholinergic (antimuscarinic) Effects

Norquetiapine, an active metabolite of quetiapine, has moderate to strong affinity for several muscarinic receptor subtypes. This contributes to anticholinergic adverse reactions when SEROQUEL XR is used at therapeutic doses, taken concomitantly with other anticholinergic medications, or taken in overdose. SEROQUEL XR should be used with caution in patients receiving medications having anticholinergic (antimuscarinic) effects [see Drug Interactions (7.1), Overdosage (10.1), and Clinical Pharmacology (12.1)].

Constipation was a commonly reported adverse event in patients treated with quetiapine and represents a risk factor for intestinal obstruction. Intestinal obstruction has been reported with quetiapine, including fatal reports in patients who were receiving multiple concomitant medications that decrease intestinal motility.

SEROQUEL XR should be used with caution in patients with a current diagnosis or prior history of urinary retention, clinically significant prostatic hypertrophy, or constipation.

6 ADVERSE REACTIONS

The following adverse reactions are discussed in more detail in other sections of the labeling:

- Increased mortality in elderly patients with dementia-related psychosis [see Warnings and Precautions (5.1)]
- Suicidal thoughts and behaviors in adolescents and young adults [see Warnings and Precautions (5.2)]
- Cerebrovascular adverse reactions, including stroke in elderly patients with dementia-related psychosis [see Warnings and Precautions (5.3)]
- Neuroleptic Malignant Syndrome (NMS) [see Warnings and Precautions (5.4)]
- Metabolic changes (hyperglycemia, dyslipidemia, weight gain) [see Warnings and Precautions (5.5)]
- Tardive dyskinesia [see Warnings and Precautions (5.6)]
- Hypotension [see Warnings and Precautions (5.7)]
- Falls [see Warnings and Precautions (5.8)]
- Increases in blood pressure (children and adolescents) [see Warnings and Precautions (5.9)]
- Leukopenia, neutropenia and agranulocytosis [see Warnings and Precautions (5.10)]
- Cataracts [see Warnings and Precautions (5.11)]
- QT Prolongation [see Warnings and Precautions (5.12)]
- Seizures [see Warnings and Precautions (5.13)]
- Hypothyroidism [see Warnings and Precautions (5.14)]
- Hyperprolactinemia [see Warnings and Precautions (5.15)]
- Potential for cognitive and motor impairment [see Warnings and Precautions (5.16)]
- Body temperature regulation [see Warnings and Precautions (5.17)]
- Dysphagia [see Warnings and Precautions (5.18)]
- Discontinuation Syndrome [see Warnings and Precautions (5.19)]
- Anticholinergic (antimuscarinic) Effects [see Warnings and Precautions, (5.20)]

6.1 Clinical Studies Experience

Because clinical trials are conducted under widely varying conditions, adverse reaction rates observed in the clinical trials of a drug cannot be directly compared to rates in the clinical trials of another drug and may not reflect the rates observed in clinical practice.

Adults

The information below is derived from a clinical trial database for SEROQUEL XR consisting of approximately 3400 patients exposed to SEROQUEL XR for the treatment of Schizophrenia, Bipolar Disorder, and Major Depressive Disorder in placebo-controlled trials. This experience corresponds to approximately 1020.1 patient-years. Adverse reactions were assessed by collecting adverse reactions, results of physical examinations, vital signs, body weights, laboratory analyses, and ECG results.

The stated frequencies of adverse reactions represent the proportion of individuals who experienced, at least once, an adverse reaction of the type listed.

Adverse Reactions Associated with Discontinuation of Treatment in Short-Term, Placebo-Controlled Trials:

Schizophrenia: There were no adverse reactions leading to discontinuation that occurred at an incidence of ≥2% for SEROQUEL XR in schizophrenia trials.

Bipolar I Disorder, Manic or Mixed Episodes:

There were no adverse reactions leading to discontinuation that occurred at an incidence of ≥2% for SEROQUEL XR in the bipolar mania trial.

Bipolar Disorder, Depressive Episode: In a single clinical trial in patients with bipolar depression, 14% (19/137) of patients on SEROQUEL XR discontinued due to an adverse reaction compared to 4% (5/140) on placebo. Somnolence2 was the only adverse reaction leading to discontinuation that occurred at an incidence of ≥2% in SEROQUEL XR in the bipolar depression trial.

MDD, Adjunctive Therapy: In adjunctive therapy clinical trials in patients with MDD, 12.1% (76/627) of patients on SEROQUEL XR discontinued due to adverse reaction compared to 1.9% (6/309) on placebo. Somnolence2 was the only adverse reaction leading to discontinuation that occurred at an incidence of ≥2% in SEROQUEL XR in MDD trials.

______________

^2Somnolence combines adverse reaction terms somnolence and sedation.

Commonly Observed Adverse Reactions in Short-Term, Placebo-Controlled Trials:

In short-term placebo-controlled studies for schizophrenia the most commonly observed adverse reactions associated with the use of SEROQUEL XR (incidence of 5% or greater) and observed at a rate on SEROQUEL XR at least twice that of placebo were somnolence (25%), dry mouth (12%), dizziness (10%), and dyspepsia (5%).

Adverse Reactions Occurring at an Incidence of 2% or More Among SEROQUEL XR Treated Patients in Short-Term, Placebo-Controlled Trials.

Table 12 enumerates the incidence, rounded to the nearest percent, of adverse reactions that occurred during acute therapy of schizophrenia (up to 6 weeks) in 2% or more in patients treated with SEROQUEL XR (doses ranging from 300 to 800 mg/day) where the incidence in patients treated with SEROQUEL XR was greater than the incidence in placebo-treated patients.

Table 12: Adverse Reactions in 6-Week Placebo-Controlled Clinical Trials for the Treatment of Schizophrenia
Preferred Term | SEROQUEL XR; (N=951) | Placebo; (N=319)
Somnolence [Somnolence combines adverse reaction terms somnolence and sedation.] | 25% | 10%
Dry Mouth | 12% | 1%
Dizziness | 10% | 4%
Extrapyramidal Symptoms [Extrapyramidal symptoms include the terms: cogwheel rigidity, drooling, dyskinesia dystonia, extrapyramidal disorder, hypertonia, movement disorder, muscle rigidity, parkinsonism, parkinsonian gait, and tardive dyskinesia.] | 8% | 5%
Orthostatic Hypotension | 7% | 5%
Constipation | 6% | 5%
Dyspepsia | 5% | 2%
Heart Rate Increased | 4% | 1%
Tachycardia | 3% | 1%
Fatigue | 3% | 2%
Hypotension | 3% | 1%
Vision Blurred | 2% | 1%
Toothache | 2% | 0%
Increased Appetite | 2% | 0%
Muscle Spasms | 2% | 1%
Tremor | 2% | 1%
Akathisia | 2% | 1%
Anxiety | 2% | 1%
Schizophrenia | 2% | 1%
Restlessness | 2% | 1%

In a 3-week, placebo-controlled study in bipolar mania the most commonly observed adverse reactions associated with the use of SEROQUEL XR (incidence of 5% or greater) and observed at a rate on SEROQUEL XR at least twice that of placebo were somnolence (50%), dry mouth (34%), dizziness (10%), constipation (10%), weight gain (7%), dysarthria (5%), and nasal congestion (5%).

Table 13 enumerates the incidence, rounded to the nearest percent, of adverse reactions that occurred during acute therapy of bipolar mania (up to 3 weeks) in 2% or more of patients treated with SEROQUEL XR (doses ranging from 400 to 800 mg/day) where the incidence in patients treated with SEROQUEL XR was greater than the incidence in placebo-treated patients.

Table 13: Adverse Reactions in a 3-Week Placebo-Controlled Clinical Trial for the Treatment of Bipolar Mania
Preferred; Term | SEROQUEL XR; (N=151) | Placebo; (N=160)
Somnolence [Somnolence combines adverse reaction terms somnolence and sedation.] | 50% | 12%
Dry Mouth | 34% | 7%
Dizziness | 10% | 4%
Constipation | 10% | 3%
Dyspepsia | 7% | 4%
Fatigue | 7% | 4%
Weight Gain | 7% | 1%
Extrapyramidal; Symptoms [Extrapyramidal symptoms include the terms: muscle spasms, akathisia, cogwheel rigidity, dystonia, extrapyramidal disorder, restlessness, and tremor.] | 7% | 4%
Nasal; Congestion | 5% | 1%
Dysarthria | 5% | 0%
Increased; Appetite | 4% | 2%
Back Pain | 3% | 2%
Toothache | 3% | 1%
Heart Rate; Increased | 3% | 0%
Abnormal; Dreams | 3% | 0%
Orthostatic; Hypotension | 3% | 0%
Tachycardia | 2% | 1%
Vision Blurred | 2% | 1%
Sluggishness | 2% | 1%
Lethargy | 2% | 1%

In the 8-week placebo-controlled bipolar depression study in adults, the most commonly observed adverse reactions associated with the use of SEROQUEL XR (incidence of 5% or greater) and observed at a rate on SEROQUEL XR at least twice that of placebo were somnolence (52%), dry mouth (37%), increased appetite (12%), weight gain (7%), dyspepsia (7%), and fatigue (6%).

Table 14 enumerates the incidence, rounded to the nearest percent, of adverse reactions that occurred during acute therapy of bipolar depression (up to 8 weeks) in 2% or more of adult patients treated with SEROQUEL XR 300 mg/day where the incidence in patients treated with SEROQUEL XR was greater than the incidence in placebo-treated patients.

Table 14: Adverse Reactions in an 8-Week Placebo-Controlled Clinical Trial for the Treatment of Bipolar Depression
Preferred Term | SEROQUEL XR; (N=137) | Placebo; (N=140)
Somnolence [Somnolence combines adverse reaction terms somnolence and sedation.] | 52% | 13%
Dry Mouth | 37% | 7%
Dizziness | 13% | 11%
Increased Appetite | 12% | 6%
Constipation | 8% | 6%
Dyspepsia | 7% | 1%
Weight Gain | 7% | 1%
Fatigue | 6% | 2%
Irritability | 4% | 3%
Viral Gastroenteritis | 4% | 1%
Arthralgia | 4% | 1%
Extrapyramidal; Symptoms [Extrapyramidal symptoms include the terms: dystonia, extrapyramidal disorder, hypertonia, and tremor.] | 4% | 1%
Paraesthesia | 3% | 2%
Back Pain | 3% | 1%
Muscle Spasms | 3% | 1%
Toothache | 3% | 0%
Abnormal Dreams | 3% | 0%
Ear Pain | 2% | 1%
Seasonal Allergy | 2% | 1%
Sinusitis | 2% | 1%
Decreased Appetite | 2% | 1%
Myalgia | 2% | 1%
Disturbance in; Attention | 2% | 1%
Migraine | 2% | 1%
Restless Legs; Syndrome | 2% | 1%
Anxiety | 2% | 1%
Sinus Headache | 2% | 1%
Libido Decreased | 2% | 1%
Pollakiuria | 2% | 1%
Sinus Congestion | 2% | 1%
Hyperhidrosis | 2% | 1%
Orthostatic Hypotension | 2% | 1%
Urinary Tract Infection | 2% | 0%
Heart Rate Increased | 2% | 0%
Neck Pain | 2% | 0%
Dysarthria | 2% | 0%
Akathisia | 2% | 0%
Hypersomnia | 2% | 0%
Mental Impairment | 2% | 0%
Confusional State | 2% | 0%
Disorientation | 2% | 0%

In the 6-week placebo-controlled fixed dose adjunctive therapy clinical trials, for MDD, the most commonly observed adverse reactions associated with the use of SEROQUEL XR (incidence of 5% or greater and observed at a rate on SEROQUEL XR and at least twice that of placebo) were somnolence (150 mg: 37%; 300 mg: 43%), dry mouth (150 mg: 27%; 300 mg: 40%), fatigue (150 mg: 14%; 300 mg: 11%), constipation (300 mg only: 11%), and weight increased (300 mg only: 5%).

Table 15 enumerates the incidence, rounded to the nearest percent, of adverse reactions that occurred during short-term adjunctive therapy of MDD (up to 6 weeks) in 2% or more of patients treated with SEROQUEL XR (at doses of either 150 mg or 300 mg/day) where the incidence in patients treated with SEROQUEL XR was greater than the incidence in placebo-treated patients.

Table 15: Adverse Reactions in Placebo-Controlled Adjunctive Therapy Clinical Trials for the Treatment of MDD by Fixed Dose
Preferred Term | SEROQUEL XR; 150 mg; (N=315) | SEROQUEL XR; 300 mg; (N=312) | Placebo; (N=309)
Somnolence [Somnolence combines the adverse reaction terms somnolence and sedation.] | 37% | 43% | 9%
Dry Mouth | 27% | 40% | 8%
Fatigue | 14% | 11% | 4%
Dizziness | 11% | 12% | 7%
Nausea | 7% | 8% | 7%
Constipation | 6% | 11% | 4%
Irritability | 4% | 2% | 3%
Extrapyramidal Symptoms [Extrapyramidal symptoms include the terms: cogwheel rigidity, drooling, dyskinesia, extrapyramidal disorder, hypertonia, hypokinesia, psychomotor hyperactivity, restlessness, and tremor.] | 4% | 6% | 4%
Vomiting | 3% | 1% | 1%
Upper Respiratory Tract Infection | 3% | 2% | 2%
Weight Increased | 3% | 5% | 0%
Increased Appetite | 3% | 5% | 3%
Back Pain | 3% | 3% | 1%
Vertigo | 2% | 2% | 1%
Vision Blurred | 2% | 1% | 1%
Dyspepsia | 2% | 3% | 2%
Influenza | 2% | 1% | 0%
Fall | 2% | 0% | 1%
Muscle Spasms | 2% | 1% | 1%
Lethargy | 2% | 1% | 1%
Akathisia | 2% | 2% | 1%
Abnormal Dreams | 2% | 2% | 1%
Anxiety | 2% | 2% | 1%
Depression | 2% | 1% | 1%

Adverse Reactions in clinical trials with quetiapine and not listed elsewhere in the label

Pyrexia, nightmares, peripheral edema, dyspnea, palpitations, rhinitis, eosinophilia, hypersensitivity, elevations in gamma-GT levels, and elevations in serum creatine phosphokinase (not associated with NMS), somnambulism (and other related events), hypothermia, decreased platelets, galactorrhea, bradycardia (which may occur at or near initiation of treatment and be associated with hypotension and/ or syncope), and priapism.

Extrapyramidal Symptoms (EPS):

Dystonia

Class Effect: Symptoms of dystonia, prolonged abnormal contractions of muscle groups, may occur in susceptible individuals during the first few days of treatment. Dystonic symptoms include: spasm of the neck muscles, sometimes progressing to tightness of the throat, swallowing difficulty, difficulty breathing, and/or protrusion of the tongue. While these symptoms can occur at low doses, they occur more frequently and with greater severity with high potency and at higher doses of first generation antipsychotic drugs. An elevated risk of acute dystonia is observed in males and younger age groups.

Four methods were used to measure EPS: (1) Simpson-Angus total score (mean change from baseline) which evaluates Parkinsonism and akathisia, (2) Barnes Akathisia Rating Scale (BARS) Global Assessment Score, (3) incidence of spontaneous complaints of EPS (akathisia, akinesia, cogwheel rigidity, extrapyramidal syndrome, hypertonia, hypokinesia, neck rigidity, and tremor), and (4) use of anticholinergic medications to treat EPS.

Adults: In placebo-controlled clinical trials with quetiapine, utilizing doses up to 800 mg per day, the incidence of any adverse reactions related to EPS ranged from 8% to 11% for quetiapine and 4% to 11% for placebo.

In three-arm placebo-controlled clinical trials for the treatment of schizophrenia, utilizing doses between 300 mg and 800 mg of SEROQUEL XR, the incidence of any adverse reactions related to EPS was 8% for SEROQUEL XR and 8% for SEROQUEL (without evidence of being dose related), and 5% in the placebo group. In these studies, the incidence of the individual adverse reactions (akathisia, extrapyramidal disorder, tremor, dyskinesia, dystonia, restlessness, and muscle rigidity) was generally low and did not exceed 3% for any treatment group.

At the end of treatment, the mean change from baseline in SAS total score and BARS Global Assessment score was similar across the treatment groups. The use of concomitant anticholinergic medications was infrequent and similar across the treatment groups. The incidence of extrapyramidal symptoms was consistent with that seen with the profile of SEROQUEL in schizophrenia patients.

In Tables 16-19, dystonic event included nuchal rigidity, hypertonia, dystonia, muscle rigidity, oculogyration; parkinsonism included cogwheel rigidity, tremor, drooling, hypokinesia; akathisia included akathisia, psychomotor agitation; dyskinetic event included tardive dyskinesia, dyskinesia, choreoathetosis; and other extrapyramidal event included restlessness, extrapyramidal disorder, movement disorder.

Table 16: Adverse Reactions Associated with Extrapyramidal Symptoms in Placebo-Controlled Clinical Trials for Schizophrenia
Preferred term | SEROQUEL XR 300 mg/day; (N=91) |  | SEROQUEL XR 400 mg/day; (N=227) |  | SEROQUEL XR 600 mg/day; (N=310) |  | SEROQUEL XR 800 mg/day; (N=323) |  | All Doses; (N=951) |  | Placebo; (N=319)
 | n | % | n | % | n | % | n | % | n | % | n | %
Dystonic event | 3 | 3.3 | 0 | 0.0 | 4 | 1.3 | 1 | 0.3 | 8 | 0.8 | 0 | 0.0
Parkinsonism | 1 | 1.1 | 3 | 1.3 | 11 | 3.6 | 7 | 2.2 | 22 | 2.3 | 4 | 1.3
Akathisia | 0 | 0.0 | 3 | 1.3 | 7 | 2.3 | 7 | 2.2 | 17 | 1.8 | 4 | 1.3
Dyskinetic event | 2 | 2.2 | 1 | 0.4 | 1 | 0.3 | 1 | 0.3 | 5 | 0.5 | 2 | 0.6
Other extrapyramidal event | 3 | 3.3 | 4 | 1.8 | 7 | 2.3 | 12 | 3.7 | 26 | 2.7 | 7 | 2.2

In a placebo-controlled clinical trial for the treatment of bipolar mania, utilizing the dose range of 400-800 mg/day of SEROQUEL XR, the incidence of any adverse reactions related to EPS was 6.6% for SEROQUEL XR and 3.8% in the placebo group. In this study, the incidence of the individual adverse reactions (akathisia, extrapyramidal disorder, tremor, dystonia, restlessness, and cogwheel rigidity) did not exceed 2.0% for any adverse reaction.

Table 17: Adverse Reactions Associated with Extrapyramidal Symptoms in a Placebo-Controlled Clinical Trial for Bipolar Mania
Preferred Term [There were no adverse reactions with the preferred term of dyskinetic event.] | SEROQUEL XR; (N=151) |  | Placebo; (N=160)
Preferred Term [There were no adverse reactions with the preferred term of dyskinetic event.] | n | % | n | %
Dystonic event | 1 | 0.7 | 0 | 0.0
Parkinsonism | 4 | 2.7 | 3 | 1.9
Akathisia | 2 | 1.3 | 1 | 0.6
Other extrapyramidal event | 3 | 2.0 | 2 | 1.3

In a placebo-controlled clinical trial for the treatment of bipolar depression utilizing 300 mg of SEROQUEL XR, the incidence of any adverse reactions related to EPS was 4.4% for SEROQUEL XR and 0.7% in the placebo group. In this study, the incidence of the individual adverse reactions (akathisia, extrapyramidal disorder, tremor, dystonia, hypertonia) did not exceed 1.5% for any individual adverse reaction.

Table 18: Adverse Reactions Associated with Extrapyramidal Symptoms in a Placebo-Controlled Clinical Trial for Bipolar Depression
Preferred Term [There were no adverse reactions with the preferred term of dyskinetic event.] | SEROQUEL XR; (N=137) |  | Placebo; (N=140)
Preferred Term [There were no adverse reactions with the preferred term of dyskinetic event.] | n | % | n | %
Dystonic event | 2 | 1.5 | 0 | 0.0
Parkinsonism | 1 | 0.7 | 1 | 0.7
Akathisia | 2 | 1.5 | 0 | 0.0
Other extrapyramidal event | 1 | 0.7 | 0 | 0.0

In two placebo-controlled short-term adjunctive therapy clinical trials for the treatment of MDD utilizing between 150 mg and 300 mg of SEROQUEL XR, the incidence of any adverse reactions related to EPS was 5.1% for SEROQUEL XR and 4.2% for the placebo group.

Table 19 shows the percentage of patients experiencing adverse reactions associated with EPS in adjunct clinical trials for MDD by dose:

Table 19: Adverse Reactions Associated with EPS in MDD Trials by Dose, Adjunctive Therapy Clinical Trials (6 weeks duration)
Preferred term | SEROQUEL XR 150 mg/day; (N=315) |  | SEROQUEL XR 300 mg/day; (N=312) |  | All Doses; (N=627) |  | Placebo; (N=309)
Preferred term | n | % | n | % | n | % | n | %
Dystonic event | 1 | 0.3 | 0 | 0.0 | 1 | 0.2 | 0 | 0.0
Parkinsonism | 3 | 1.0 | 4 | 1.3 | 7 | 1.1 | 5 | 1.6
Akathisia | 5 | 1.6 | 8 | 2.6 | 13 | 2.1 | 3 | 1.0
Dyskinetic event | 0 | 0.0 | 1 | 0.3 | 1 | 0.2 | 0 | 0.0
Other extrapyramidal event | 5 | 1.6 | 7 | 2.2 | 12 | 1.9 | 5 | 1.6

Children and Adolescents

The information below is derived from a clinical trial database for SEROQUEL consisting of over 1000 pediatric patients. This database includes 677 adolescents (13-17 years old) exposed to SEROQUEL for the treatment of schizophrenia and 393 children and adolescents (10-17 years old) exposed to SEROQUEL for the treatment of acute bipolar mania.

Adverse Reactions Associated with Discontinuation of Treatment in Short-Term, Placebo-Controlled Trials:

Schizophrenia: The incidence of discontinuation due to adverse reactions for quetiapine-treated and placebo-treated patients was 8.2% and 2.7%, respectively. The adverse reaction leading to discontinuation in 2% or more of patients on quetiapine and at a greater incidence than placebo was somnolence (2.7% and 0% for placebo).

Bipolar I Mania: The incidence of discontinuation due to adverse reactions for quetiapine-treated and placebo-treated patients was 11.4% and 4.4%, respectively. The adverse reactions leading to discontinuation in 2% or more of patients on SEROQUEL and at a greater incidence than placebo were somnolence (4.1% vs. 1.1%) and fatigue (2.1% vs. 0%).

Commonly Observed Adverse Reactions in Short-Term, Placebo-Controlled Trials:

In an acute (8-week) SEROQUEL XR trial in children and adolescents (10-17 years of age) with bipolar depression, in which efficacy was not established, the most commonly observed adverse reactions associated with the use of SEROQUEL XR (incidence of 5% or greater and at least twice that for placebo) were: dizziness (7%), diarrhea (5%), fatigue (5%) and nausea (5%).

In therapy for schizophrenia (up to 6 weeks), the most commonly observed adverse reactions associated with the use of quetiapine in adolescents (incidence of 5% or greater and quetiapine incidence at least twice that for placebo) were somnolence (34%), dizziness (12%), dry mouth (7%), tachycardia (7%).

In bipolar mania therapy (up to 3 weeks) the most commonly observed adverse reactions associated with the use of quetiapine in children and adolescents (incidence of 5% or greater and quetiapine incidence at least twice that for placebo) were somnolence (53%), dizziness (18%), fatigue (11%), increased appetite (9%), nausea (8%), vomiting (8%), tachycardia (7%), dry mouth (7%), and weight increased (6%).

Adverse Reactions Occurring at an Incidence of ≥2% among SEROQUEL Treated Patients in Short-Term, Placebo-Controlled Trials

Schizophrenia (Adolescents, 13-17 years old)

The following findings were based on a 6-week placebo-controlled trial in which quetiapine was administered in either doses of 400 or 800 mg/day.

Table 20 enumerates the incidence, rounded to the nearest percent, of adverse reactions that occurred during therapy (up to 6 weeks) of schizophrenia in 2% or more of patients treated with SEROQUEL (doses of 400 or 800 mg/day) where the incidence in patients treated with SEROQUEL was greater than the incidence in placebo-treated patients.

Adverse reactions that were potentially dose-related with higher frequency in the 800 mg group compared to the 400 mg group included dizziness (8% vs. 15%), dry mouth (4% vs. 10%), and tachycardia (6% vs. 11%).

Table 20: Adverse Reactions in a 6-Week Placebo-Controlled Clinical Trial for the Treatment of Schizophrenia in Adolescent Patients
Preferred Term | SEROQUEL 400 mg; (N=73) | SEROQUEL 800 mg; (N=74) | Placebo; (N=75)
Somnolence [Somnolence combines adverse reaction terms somnolence and sedation.] | 33% | 35% | 11%
Dizziness | 8% | 15% | 5%
Dry Mouth | 4% | 10% | 1%
Tachycardia [Tachycardia combines adverse reaction terms tachycardia and sinus tachycardia.] | 6% | 11% | 0%
Irritability | 3% | 5% | 0%
Arthralgia | 1% | 3% | 0%
Asthenia | 1% | 3% | 1%
Back Pain | 1% | 3% | 0%
Dyspnea | 0% | 3% | 0%
Abdominal Pain | 3% | 1% | 0%
Anorexia | 3% | 1% | 0%
Tooth Abscess | 3% | 1% | 0%
Dyskinesia | 3% | 0% | 0%
Epistaxis | 3% | 0% | 1%
Muscle Rigidity | 3% | 0% | 0%

Bipolar I Mania (Children and Adolescents 10 to 17 years old)

The following findings were based on a 3-week placebo-controlled trial in which quetiapine was administered in either doses of 400 or 600 mg/day.

Table 21 enumerates the incidence, rounded to the nearest percent, of adverse reactions that occurred during therapy (up to 3 weeks) of bipolar mania in 2% or more of patients treated with SEROQUEL (doses of 400 or 600 mg/day) where the incidence in patients treated with SEROQUEL was greater than the incidence in placebo-treated patients.

Adverse reactions that were potentially dose-related with higher frequency in the 600 mg group compared to the 400 mg group included somnolence (50% vs. 57%), nausea (6% vs. 10%), and tachycardia (6% vs. 9%).

Table 21: Adverse Reactions in a 3-Week Placebo-Controlled Clinical Trial for the Treatment of Bipolar Mania in Children and Adolescent Patients
Preferred Term | SEROQUEL 400 mg; (N=95) | SEROQUEL 600 mg; (N=98) | Placebo; (N=90)
Somnolence [Somnolence combines adverse reaction terms somnolence and sedation.] | 50% | 57% | 14%
Dizziness | 19% | 17% | 2%
Nausea | 6% | 10% | 4%
Fatigue | 14% | 9% | 4%
Increased Appetite | 10% | 9% | 1%
Tachycardia [Tachycardia combines adverse reaction terms tachycardia and sinus tachycardia.] | 6% | 9% | 0%
Dry Mouth | 7% | 7% | 0%
Vomiting | 8% | 7% | 3%
Nasal Congestion | 3% | 6% | 2%
Weight Increased | 6% | 6% | 0%
Irritability | 3% | 5% | 1%
Pyrexia | 1% | 4% | 1%
Aggression | 1% | 3% | 0%
Musculoskeletal; Stiffness | 1% | 3% | 1%
Accidental Overdose | 0% | 2% | 0%
Acne | 3% | 2% | 0%
Arthralgia | 4% | 2% | 1%
Lethargy | 2% | 2% | 0%
Pallor | 1% | 2% | 0%
Stomach; Discomfort | 4% | 2% | 1%
Syncope | 2% | 2% | 0%
Vision Blurred | 3% | 2% | 0%
Constipation | 4% | 2% | 0%
Ear Pain | 2% | 0% | 0%
Paresthesia | 2% | 0% | 0%
Sinus Congestion | 3% | 0% | 0%
Thirst | 2% | 0% | 0%

Extrapyramidal Symptoms:

Safety and effectiveness of SEROQUEL XR is supported by studies of SEROQUEL in children and adolescent patients 10-17 years of age [see Clinical Studies (14.1 and 14.2)].

In a short-term placebo-controlled SEROQUEL XR monotherapy trial in children and adolescent patients (10-17 years of age) with bipolar depression (8-week duration), in which efficacy was not established, the aggregated incidence of extrapyramidal symptoms was 1.1% (1/92) for SEROQUEL XR and 0% (0/100) for placebo.

In a short-term placebo-controlled SEROQUEL monotherapy trial in adolescent patients (13-17 years of age) with schizophrenia (6-week duration), the aggregated incidence of extrapyramidal symptoms was 12.9% (19/147) for SEROQUEL and 5.3% (4/75) for placebo, though the incidence of the individual adverse reactions (e.g., akathisia, tremor, extrapyramidal disorder, hypokinesia, restlessness, psychomotor hyperactivity, muscle rigidity, dyskinesia) did not exceed 4.1% in any treatment group. In a short-term placebo-controlled SEROQUEL monotherapy trial in children and adolescent patients (10-17 years of age) with bipolar mania (3-week duration), the aggregated incidence of extrapyramidal symptoms was 3.6% (7/193) for SEROQUEL and 1.1% (1/90) for placebo.

In Tables 22 and 23, dystonic events included nuchal rigidity, hypertonia, dystonia, and muscle rigidity; parkinsonism included cogwheel rigidity and tremor; akathisia included akathisia only; dyskinetic event included tardive dyskinesia, dyskinesia and choreoathetosis; and other extrapyramidal event included restlessness and extrapyramidal disorder.

Table 22 below presents a listing of patients with adverse reactions associated with EPS in the short-term placebo-controlled SEROQUEL monotherapy trial in adolescent patients with schizophrenia (6-week duration).

Table 22: Adverse Reactions Associated with Extrapyramidal Symptoms in the Placebo-Controlled Trial in Adolescent Patients with Schizophrenia (6-week duration)
Preferred term | SEROQUEL; 400 mg/day; (N=73) |  | SEROQUEL; 800 mg/day; (N=74) |  | All SEROQUEL; (N=147) |  | Placebo; (N=75)
Preferred term | n | % | n | % | n | % | n | %
Dystonic Event | 2 | 2.7 | 0 | 0.0 | 2 | 1.4 | 0 | 0.0
Parkinsonism | 4 | 5.5 | 4 | 5.4 | 8 | 5.4 | 2 | 2.7
Akathisia | 3 | 4.1 | 4 | 5.4 | 7 | 4.8 | 3 | 4.0
Dyskinetic Event | 2 | 2.7 | 0 | 0.0 | 2 | 1.4 | 0 | 0.0
Other Extrapyramidal Event | 2 | 2.7 | 2 | 2.7 | 4 | 2.7 | 0 | 0.0

Table 23 below presents a listing of patients with adverse reactions associated with EPS in a short-term placebo-controlled monotherapy trial in children and adolescent patients with bipolar mania (3-week duration).

Table 23: Adverse Reactions Associated with Extrapyramidal Symptoms in a Placebo-Controlled Trial in Children and Adolescent Patients with Bipolar I Mania (3-week duration)
Preferred Term [There were no adverse reactions with the preferred term of dystonic or dyskinetic events.] | SEROQUEL; 400 mg/day; (N=95) |  | SEROQUEL; 600 mg/day; (N=98) |  | All SEROQUEL; (N=193) |  | Placebo; (N=90)
Preferred Term [There were no adverse reactions with the preferred term of dystonic or dyskinetic events.] | n | % | n | % | n | % | n | %
Parkinsonism | 2 | 2.1 | 1 | 1.0 | 3 | 1.6 | 1 | 1.1
Akathisia | 1 | 1.0 | 1 | 1.0 | 2 | 1.0 | 0 | 0.0
Other Extrapyramidal Event | 1 | 1.1 | 1 | 1.0 | 2 | 1.0 | 0 | 0.0

Laboratory, ECG and vital sign changes observed in clinical studies

Laboratory Changes:

Neutrophil Counts

Adults: In three-arm SEROQUEL XR placebo-controlled monotherapy clinical trials, among patients with a baseline neutrophil count ≥1.5 x 10^9/L, the incidence of at least one occurrence of neutrophil count <1.5 x 10^9/L was 1.5% in patients treated with SEROQUEL XR and 1.5% for SEROQUEL, compared to 0.8% in placebo-treated patients.

In placebo-controlled monotherapy clinical trials involving 3368 patients on quetiapine and 1515 on placebo, the incidence of at least one occurrence of neutrophil count <1.0 x 10^9/L among patients with a normal baseline neutrophil count and at least one available follow up laboratory measurement was 0.3% (10/2967) in patients treated with quetiapine, compared to 0.1% (2/1349) in patients treated with placebo [see Warnings and Precautions (5.10)].

Transaminase Elevations

Adults: Asymptomatic, transient and reversible elevations in serum transaminases (primarily ALT) have been reported. The proportions of adult patients with transaminase elevations of >3 times the upper limits of the normal reference range in a pool of placebo-controlled trials ranged between 1% and 2% for SEROQUEL XR compared to 2% for placebo. In schizophrenia trials in adults, the proportions of patients with transaminase elevations of >3 times the upper limits of the normal reference range in a pool of 3- to 6-week placebo-controlled trials were approximately 6% (29/483) for SEROQUEL compared to 1% (3/194) for placebo. These hepatic enzyme elevations usually occurred within the first 3 weeks of drug treatment and promptly returned to pre-study levels with ongoing treatment with quetiapine.

Decreased Hemoglobin

Adults: In short-term placebo-controlled trials, decreases in hemoglobin to ≤13 g/dL males, ≤12 g/dL females on at least one occasion occurred in 8.3% (594/7155) of quetiapine-treated patients compared to 6.2% (219/3536) of patients treated with placebo. In a database of controlled and uncontrolled clinical trials, decreases in hemoglobin to ≤13 g/dL males, ≤12 g/dL females on at least one occasion occurred in 11% (2277/20729) of quetiapine-treated patients.

Interference with Urine Drug Screens

There have been literature reports suggesting false positive results in urine enzyme immunoassays for methadone and tricyclic antidepressants in patients who have taken quetiapine. Caution should be exercised in the interpretation of positive urine drug screen results for these drugs, and confirmation by alternative analytical technique (e.g., chromatographic methods) should be considered.

ECG Changes:

Adults: 2.5% of SEROQUEL XR patients, and 2.3% of placebo patients, had tachycardia (>120 bpm) at any time during the trials. SEROQUEL XR was associated with a mean increase in heart rate, assessed by ECG, of 6.3 beats per minute compared to a mean increase of 0.4 beats per minute for placebo. This is consistent with the rates for SEROQUEL. The incidence of adverse reactions of tachycardia was 1.9% for SEROQUEL XR compared to 0.5% for placebo. SEROQUEL use was associated with a mean increase in heart rate, assessed by ECG, of 7 beats per minute compared to a mean increase of 1 beat per minute among placebo patients. The slight tendency for tachycardia may be related to quetiapine’s potential for inducing orthostatic changes [see Warnings and Precautions (5.7)].

Children and Adolescents: Safety and effectiveness of SEROQUEL XR is supported by studies of SEROQUEL in children and adolescent patients 10-17 years of age [see Clinical Studies (14.1 and 14.2)].

In an acute (8-week) SEROQUEL XR trial in children and adolescents (10-17 years of age) with bipolar depression, in which efficacy was not established, increases in heart rate (>110 bpm 10-12 years and 13-17 years) occurred in 0% of patients receiving SEROQUEL XR and 1.2% of patients receiving placebo. Mean increases in heart rate were 3.4 bpm for SEROQUEL XR, compared to 0.3 bpm in the placebo group [see Warnings and Precautions (5.7)].

In the acute (6-week) SEROQUEL schizophrenia trial in adolescents (13-17 years of age), increases in heart rate (>110 bpm) occurred in 5.2% of patients receiving SEROQUEL 400 mg and 8.5% of patients receiving SEROQUEL 800 mg compared to 0% of patients receiving placebo. Mean increases in heart rate were 3.8 bpm and 11.2 bpm for SEROQUEL 400 mg and 800 mg groups, respectively, compared to a decrease of 3.3 bpm in the placebo group [see Warnings and Precautions (5.7)].

In the acute (3-week) SEROQUEL bipolar mania trial in children and adolescents (10-17 years of age), increases in heart rate (>110 bpm) occurred in 1.1% of patients receiving SEROQUEL 400 mg and 4.7% of patients receiving SEROQUEL 600 mg compared to 0% of patients receiving placebo. Mean increases in heart rate were 12.8 bpm and 13.4 bpm for SEROQUEL 400 mg and 600 mg groups, respectively, compared to a decrease of 1.7 bpm in the placebo group [see Warnings and Precautions (5.7)].

6.2 Postmarketing Experience

The following adverse reactions were identified during post approval use of SEROQUEL. Because these reactions are reported voluntarily from a population of uncertain size, it is not always possible to reliably estimate their frequency or establish a causal relationship to drug exposure.

Adverse reactions reported since market introduction which were temporally related to quetiapine therapy include anaphylactic reaction, cardiomyopathy, drug reaction with eosinophilia and systemic symptoms (DRESS), hyponatremia, myocarditis, nocturnal enuresis, pancreatitis, retrograde amnesia, rhabdomyolysis, syndrome of inappropriate antidiuretic hormone secretion (SIADH), Stevens-Johnson syndrome (SJS), toxic epidermal necrolysis (TEN), decreased platelet count, serious liver reactions (including hepatitis, liver necrosis, and hepatic failure), agranulocytosis, intestinal obstruction, ileus, colon ischemia, sleep apnea, urinary retention, acute generalized exanthematous pustulosis (AGEP), confusional state, cutaneous vasculitis, and fecal incontinence. Bezoar observed in overdosage [see Overdosage (10)].

7 DRUG INTERACTIONS

7.1 Effect of Other Drugs on Quetiapine

The risks of using SEROQUEL XR in combination with other drugs have not been extensively evaluated in systematic studies. Given the primary CNS effects of SEROQUEL XR, caution should be used when it is taken in combination with other centrally acting drugs. Quetiapine potentiated the cognitive and motor effects of alcohol in a clinical trial in subjects with selected psychotic disorders, and alcoholic beverages should be limited while taking quetiapine.

Quetiapine exposure is increased by the prototype CYP3A4 inhibitors (e.g., ketoconazole, itraconazole, indinavir, ritonavir, nefazodone, etc.) and decreased by the prototype of CYP3A4 inducers (e.g., phenytoin, carbamazepine, rifampin, avasimibe, St. John’s wort etc.). Dose adjustment of quetiapine will be necessary if it is co-administered with potent CYP3A4 inducers or inhibitors.

CYP3A4 inhibitors:

Coadministration of ketoconazole, a potent inhibitor of cytochrome CYP3A4, resulted in significant increase in quetiapine exposure. The dose should be reduced to one‑sixth of the original dose in patients coadministered with a strong CYP3A4 inhibitor [see Dosage and Administration (2.5) and Clinical Pharmacology (12.3)].

CYP3A4 inducers:

Coadministration of quetiapine and phenytoin, a CYP3A4 inducer increased the mean oral clearance of quetiapine by 5-fold. Increased doses of SEROQUEL XR up to 5-fold may be required to maintain control of symptoms of schizophrenia in patients receiving quetiapine and phenytoin, or other known potent CYP3A4 inducers [see Dosage and Administration (2.6) and Clinical Pharmacology (12.3)]. When the CYP3A4 inducer is discontinued, the dose of SEROQUEL XR should be reduced to the original level within 7-14 days [see Dosage and Administration (2.6)].

Anticholinergic Drugs:

Concomitant treatment with quetiapine and other drugs with anticholinergic activity can increase the risk for severe gastrointestinal adverse reactions related to hypomotility. SEROQUEL should be used with caution in patients receiving medications having anticholinergic (antimuscarinic) effects [see Warnings and Precautions (5.20)].

The potential effects of several concomitant medications on quetiapine pharmacokinetics were studied [see Clinical Pharmacology (12.3)].

7.2 Effect of Quetiapine on Other Drugs

Because of its potential for inducing hypotension, SEROQUEL XR may enhance the effects of certain antihypertensive agents.

SEROQUEL XR may antagonize the effects of levodopa and dopamine agonists.

There are no clinically relevant pharmacokinetic interactions of Seroquel on other drugs based on the CYP pathway. Seroquel and its metabolites are non-inhibitors of major metabolizing CYP’s (1A2, 2C9, 2C19, 2D6, and 3A4).

8 USE IN SPECIFIC POPULATIONS

8.1 Pregnancy

Pregnancy Exposure Registry

There is a pregnancy exposure registry that monitors pregnancy outcomes in women exposed to atypical antipsychotics, including SEROQUEL XR, during pregnancy. Healthcare providers are encouraged to register patients by contacting the National Pregnancy Registry for Atypical Antipsychotics at 1-866-961-2388 or online at http://womensmentalhealth.org/clinical-and-research-programs/pregnancyregistry/

Risk Summary

Neonates exposed to antipsychotic drugs, including SEROQUEL XR, during the third trimester are at risk for extrapyramidal and/or withdrawal symptoms following delivery (see Clinical Considerations). Overall available data from published epidemiologic studies of pregnant women exposed to quetiapine have not established a drug-associated risk of major birth defects, miscarriage, or adverse maternal or fetal outcomes (see Data). There are risks to the mother associated with untreated schizophrenia, bipolar I, or major depressive disorder, and with exposure to antipsychotics, including, SEROQUEL XR during pregnancy (see Clinical Considerations). In animal studies, embryo-fetal toxicity occurred including delays in skeletal ossification at approximately 1 and 2 times the maximum recommended human dose (MRHD) of 800 mg/day in both rats and rabbits, and an increased incidence of carpal/tarsal flexure (minor soft tissue anomaly) in rabbit fetuses at approximately 2 times the MRHD. In addition, fetal weights were decreased in both species. Maternal toxicity (observed as decreased body weights and/or death) occurred at 2 times the MRHD in rats and approximately 1-2 times the MRHD in rabbits.

The estimated background risk of major birth defects and miscarriage for the indicated populations is unknown. All pregnancies have a background risk of birth defect, loss, or other adverse outcomes. In the U.S. general population, the estimated background risk of major birth defects and miscarriage in clinically recognized pregnancies is 2 to 4% and 15 to 20%, respectively.

Clinical Considerations

Disease-associated maternal and/or fetal risk

There is a risk to the mother from untreated schizophrenia, or bipolar I disorder, including increased risk of relapse, hospitalization, and suicide. Schizophrenia and bipolar I disorder are associated with increased adverse perinatal outcomes, including preterm birth. It is not known if this is a direct result of the illness or other comorbid factors.

A prospective, longitudinal study followed 201 pregnant women with a history of major depressive disorder who were euthymic and taking antidepressants at the beginning of pregnancy. The women who discontinued antidepressants during pregnancy were more likely to experience a relapse of major depression than women who continued antidepressants. Consider the risk of untreated depression when discontinuing or changing treatment with antidepressant medication during pregnancy and postpartum.

Fetal/neonatal adverse reactions

Extrapyramidal and/or withdrawal symptoms, including agitation, hypertonia, hypotonia, tremor, somnolence, respiratory distress, and feeding disorder have been reported in neonates who were exposed to antipsychotic drugs, including SEROQUEL XR, during the third trimester of pregnancy. These symptoms varied in severity. Monitor neonates for extrapyramidal and/or withdrawal symptoms and manage symptoms appropriately. Some neonates recovered within hours or days without specific treatment; others required prolonged hospitalization.

Data

Human Data

Published data from observational studies, birth registries, and case reports on the use of atypical antipsychotics during pregnancy do not report a clear association with antipsychotics and major birth defects. A retrospective cohort study from a Medicaid database of 9258 women exposed to antipsychotics during pregnancy did not indicate an overall increased risk of major birth defects.

Animal Data

When pregnant rats and rabbits were exposed to quetiapine during organogenesis, there was no teratogenic effect in fetuses. Doses were 25, 50 and 200 mg/kg in rats and 25, 50 and 100 mg/kg in rabbits which are approximately 0.3, 0.6 and 2-times (rats) and 0.6, 1 and 2-times (rabbits) the MRHD, for schizophrenia of 800 mg/day based on mg/m^2 body surface area. However, there was evidence of embryo-fetal toxicity, including delays in skeletal ossification at approximately 1 and 2 times the MRHD of 800 mg/day in both rats and rabbits and an increased incidence of carpal/tarsal flexure (minor soft tissue anomaly) in rabbit fetuses at approximately 2 times the MRHD. In addition, fetal weights were decreased in both species. Maternal toxicity (observed as decreased body weights and/or death) occurred at 2 times the MRHD in rats and at approximately 1-2 times the MRHD (all doses tested) in rabbits.

In a peri/postnatal reproductive study in rats, no drug-related effects were observed when pregnant dams were treated with quetiapine at doses 0.01, 0.1, and 0.2 times the MRHD of 800 mg/day based on mg/m^2 body surface area. However, in a preliminary peri/postnatal study, there were increases in fetal and pup death, and decreases in mean litter weight at 3 times the MRHD.

8.2 Lactation

Risk Summary

Limited data from published literature report the presence of quetiapine in human breast milk at relative infant dose of <1% of the maternal weight-adjusted dosage. There are no consistent adverse events that have been reported in infants exposed to quetiapine through breast milk. There is no information on the effects of quetiapine on milk production. The developmental and health benefits of breastfeeding should be considered along with the mother’s clinical need for SEROQUEL XR and any potential adverse effects on the breastfed child from SEROQUEL XR or from the mother’s underlying condition.

8.3 Females and Males of Reproductive Potential

Infertility

Females

Based on the pharmacologic action of quetiapine (D2 antagonism), treatment with SEROQUEL XR may result in an increase in serum prolactin levels, which may lead to a reversible reduction in fertility in females of reproductive potential [see Warnings and Precautions (5.15)].

8.4 Pediatric Use

Safety and effectiveness of SEROQUEL XR is supported by studies of SEROQUEL for schizophrenia in adolescent patients 13 - 17 years of age and in bipolar mania in children and adolescent patients 10 - 17 years of age [see Clinical Studies (14.1 and 14.2)].

In general, the adverse reactions observed in children and adolescents during the clinical trials with SEROQUEL were similar to those in the adult population with few exceptions. Increases in systolic and diastolic blood pressure occurred in children and adolescents and did not occur in adults. Orthostatic hypotension occurred more frequently in adults (4-7%) compared to children and adolescents (<1%) [see Warnings and Precautions (5.7) and Adverse Reactions (6.1)].

Bipolar Depression

The effectiveness of SEROQUEL XR for the treatment of bipolar depression in patients under the age of 18 years has not been established. One 8-week trial was conducted to evaluate the safety and efficacy of SEROQUEL XR in the treatment of bipolar depression in pediatric patients 10 - 17 years of age. The primary objective of the study was to evaluate whether SEROQUEL XR at a dose of 150 to 300 mg/day demonstrated superior efficacy (as measured by change in CDRS-R total score from baseline to end of 8 weeks) compared to placebo in children and adolescents 10 - 17 years of age with bipolar depression. A total of 193 patients with bipolar depression were randomized to placebo or SEROQUEL XR. The primary results of this study did not show a difference between SEROQUEL XR and placebo in decreasing depression symptoms in children and adolescents with bipolar disorder. In this study, patients treated with SEROQUEL XR exhibited metabolic changes, weight gain, increases in blood pressure and increases in heart rate [see Warnings and Precautions (5.5, 5.9) and Adverse Reactions (6.1)].

Some differences in the pharmacokinetics of quetiapine were noted between children/adolescents (10 - 17 years of age) and adults. When adjusted for weight, the AUC and Cmax of quetiapine were 41% and 39% lower, respectively, in children and adolescents compared to adults. The pharmacokinetics of the active metabolite, norquetiapine, were similar between children/adolescents and adults after adjusting for weight [see Clinical Pharmacology (12.3)].

Schizophrenia

The efficacy and safety of SEROQUEL XR in the treatment of schizophrenia in adolescents aged 13 - 17 years is supported by one 6-week, double-blind, placebo-controlled trial with SEROQUEL [see Indications and Usage (1.1), Dosage and Administration (2.2), Adverse Reactions (6.1), and Clinical Studies (14.1)].

Safety and effectiveness of SEROQUEL XR in pediatric patients less than 13 years of age with schizophrenia have not been established.

The safety and effectiveness of SEROQUEL XR in the maintenance treatment of schizophrenia has not been established in patients less than 18 years of age.

Bipolar Mania

The efficacy and safety of SEROQUEL XR in the treatment of bipolar mania in children and adolescents ages 10-17 years is supported by one 3-week, double-blind, placebo‑controlled trial with SEROQUEL [see Indications and Usage (1.2), Dosage and Administration (2.2), Adverse Reactions (6.1), and Clinical Studies (14.2)].

Safety and effectiveness of SEROQUEL XR in pediatric patients less than 10 years of age with bipolar mania have not been established.

The safety and effectiveness of SEROQUEL XR in the maintenance treatment of bipolar disorder has not been established in patients less than 18 years of age.

8.5 Geriatric Use

Sixty-eight patients in clinical studies with SEROQUEL XR were 65 years of age or over. In general, there was no indication of any different tolerability of SEROQUEL XR in the elderly compared to younger adults. Nevertheless, the presence of factors that might decrease pharmacokinetic clearance, increase the pharmacodynamic response to SEROQUEL XR, or cause poorer tolerance or orthostasis, should lead to consideration of a lower starting dose, slower titration, and careful monitoring during the initial dosing period in the elderly. The mean plasma clearance of quetiapine was reduced by 30% to 50% in elderly patients when compared to younger patients [see Dosage and Administration (2.3) and Clinical Pharmacology (12.3)].

8.6 Renal Impairment

Clinical experience with SEROQUEL XR in patients with renal impairment is limited [see Clinical Pharmacology (12.3)].

8.7 Hepatic Impairment

Since quetiapine is extensively metabolized by the liver, higher plasma levels are expected in patients with hepatic impairment. In this population, a low starting dose of 50 mg/day is recommended and the dose may be increased in increments of 50 mg/day [see Dosage and Administration (2.4) and Clinical Pharmacology (12.3)].

9 DRUG ABUSE AND DEPENDENCE

9.1 Controlled Substance

SEROQUEL XR is not a controlled substance.

9.2 Abuse

SEROQUEL XR has not been systematically studied in animals or humans for its potential for abuse, tolerance, or physical dependence. While the clinical trials did not reveal any tendency for any drug-seeking behavior, these observations were not systematic and it is not possible to predict on the basis of this limited experience the extent to which a CNS-active drug will be misused, diverted, and/or abused once marketed. Consequently, patients should be evaluated carefully for a history of drug abuse, and such patients should be observed closely for signs of misuse or abuse of SEROQUEL XR (e.g., development of tolerance, increases in dose, drug-seeking behavior).

10 OVERDOSAGE

10.1 Human Experience

In clinical trials, survival has been reported in acute overdoses of up to 30 grams of quetiapine. Most patients who overdosed experienced no adverse reactions or recovered fully from the reported events. Death has been reported in a clinical trial following an overdose of 13.6 grams of quetiapine alone. In general, reported signs and symptoms were those resulting from an exaggeration of the drug’s known pharmacological effects, i.e., drowsiness, sedation, tachycardia, hypotension, and anticholinergic toxicity including coma and delirium. Patients with pre-existing severe cardiovascular disease may be at an increased risk of the effects of overdose [see Warnings and Precautions (5.12)]. One case, involving an estimated overdose of 9600 mg, was associated with hypokalemia and first degree heart block. In post-marketing experience, there were cases reported of QT prolongation with overdose.

10.2 Management of Overdosage

Establish and maintain an airway and ensure adequate oxygenation and ventilation. Cardiovascular monitoring should commence immediately and should include continuous electrocardiographic monitoring to detect possible arrhythmias.

Appropriate supportive measures are the mainstay of management. For the most up-to-date information on the management of Seroquel XR overdosage, contact a certified Regional Poison Control Center (1-800-222-1222).

SEROQUEL XR overdose may lead to gastric bezoar formation and appropriate diagnostic imaging is recommended to further guide patient management. Routine gastric lavage may not be effective in the removal of the bezoar due to gum like sticky consistency of the mass. Endoscopic pharmacobezoar removal has been performed successfully.

11 DESCRIPTION

SEROQUEL XR (quetiapine) is an atypical antipsychotic belonging to a chemical class, the dibenzothiazepine derivatives. The chemical designation is 2-[2-(4-dibenzo [b,f ] [1,4] thiazepin-11-yl-1-piperazinyl)ethoxy]-ethanol fumarate (2:1) (salt). It is present in tablets as the fumarate salt. All doses and tablet strengths are expressed as milligrams of base, not as fumarate salt. Its molecular formula is C42H50N6O4S2•C4H4O4 and it has a molecular weight of 883.11 (fumarate salt). The structural formula is:

Quetiapine fumarate is a white to off-white crystalline powder which is moderately soluble in water.

SEROQUEL XR is supplied for oral administration as 50 mg (peach), 150 mg (white), 200 mg (yellow), 300 mg (pale yellow), and 400 mg (white). All tablets are capsule shaped and film coated.

Inactive ingredients for SEROQUEL XR are lactose monohydrate, microcrystalline cellulose, sodium citrate, hypromellose, and magnesium stearate. The film coating for all SEROQUEL XR tablets contain hypromellose, polyethylene glycol 400 and titanium dioxide. In addition, yellow iron oxide (50, 200 and 300 mg tablets) and red iron oxide (50 mg tablets) are included in the film coating of specific strengths.

Each 50 mg tablet contains 57.56 mg of quetiapine fumarate equivalent to 50 mg quetiapine. Each 150 mg tablet contains 172.69 mg of quetiapine fumarate equivalent to 150 mg quetiapine. Each 200 mg tablet contains 230.26 mg of quetiapine fumarate equivalent to 200 mg quetiapine. Each 300 mg tablet contains 345.38 mg of quetiapine fumarate equivalent to 300 mg quetiapine. Each 400 mg tablet contains 460.50 mg of quetiapine fumarate equivalent to 400 mg quetiapine.

12 CLINICAL PHARMACOLOGY

12.1 Mechanism of Action

The mechanism of action of quetiapine in the listed indications is unclear. However, the efficacy of quetiapine in these indications could be mediated through a combination of dopamine type 2 (D2) and serotonin type 2A (5HT2A) antagonism. The active metabolite, N-desalkyl quetiapine (norquetiapine), has similar activity at D2, but greater activity at 5HT2A receptors, than the parent drug (quetiapine).

12.2 Pharmacodynamics

Quetiapine and its metabolite norquetiapine have affinity for multiple neurotransmitter receptors with norquetiapine binding with higher affinity than quetiapine in general. The Ki values for quetiapine and norquetiapine at the dopamine D1 are 428/99.8 nM, at D2 626/489nM, at serotonin 5HT1A 1040/191 nM at 5HT2A 38/2.9 nM, at histamine H1 4.4/1.1 nM, at muscarinic M1 1086/38.3 nM, and at adrenergic α1b 14.6/46.4 nM and, at α2 receptors 617/1290 nM, respectively. Quetiapine and norquetiapine lack appreciable affinity to the benzodiazepine receptors.

Effect on QT Interval

In clinical trials quetiapine was not associated with a persistent increase in QT intervals. However, the QT effect was not systematically evaluated in a thorough QT study. In post marketing experience, there were cases reported of QT prolongation in patients who overdosed on quetiapine [see Overdosage (10.1)], in patients with concomitant illness, and in patients taking medicines known to cause electrolyte imbalance or increase QT interval.

12.3 Pharmacokinetics

Adults

Following multiple dosing of quetiapine up to a total daily dose of 800 mg, administered in divided doses, the plasma concentration of quetiapine and norquetiapine, the major active metabolite of quetiapine, were proportional to the total daily dose. Accumulation is predictable upon multiple dosing. Steady-state mean Cmax and AUC of norquetiapine are about 21-27% and 46-56%, respectively, of that observed for quetiapine. Elimination of quetiapine is mainly via hepatic metabolism. The mean-terminal half-life is approximately 7 hours for quetiapine and approximately 12 hours for norquetiapine within the clinical dose range. Steady-state concentrations are expected to be achieved within two days of dosing. SEROQUEL XR is unlikely to interfere with the metabolism of drugs metabolized by cytochrome P450 enzymes.

Children and Adolescents

At steady state, the pharmacokinetics of the parent compound, in children and adolescents (10-17 years of age), were similar to adults. However, when adjusted for dose and weight, AUC and Cmax of the parent compound were 41% and 39% lower, respectively, in children and adolescents than in adults. For the active metabolite, norquetiapine, AUC and Cmax were 45% and 31% higher, respectively, in children and adolescents than in adults. When adjusted for dose and weight, the pharmacokinetics of the metabolite, norquetiapine, was similar between children and adolescents and adults [see Use in Specific Populations (8.4)].

Absorption

Quetiapine reaches peak plasma concentrations approximately 6 hours following administration. SEROQUEL XR dosed once daily at steady state has comparable bioavailability to an equivalent total daily dose of SEROQUEL administered in divided doses, twice daily. A high-fat meal (approximately 800 to 1000 calories) was found to produce statistically significant increases in the SEROQUEL XR Cmax and AUC of 44% to 52% and 20% to 22%, respectively, for the 50 mg and 300 mg tablets. In comparison, a light meal (approximately 300 calories) had no significant effect on the Cmax or AUC of quetiapine. It is recommended that SEROQUEL XR be taken without food or with a light meal [see Dosage and Administration (2.1)].

Distribution

Quetiapine is widely distributed throughout the body with an apparent volume of distribution of 10±4 L/kg. It is 83% bound to plasma proteins at therapeutic concentrations. In vitro, quetiapine did not affect the binding of warfarin or diazepam to human serum albumin. In turn, neither warfarin nor diazepam altered the binding of quetiapine.

Metabolism and Elimination

Following a single oral dose of ^14C-quetiapine, less than 1% of the administered dose was excreted as unchanged drug, indicating that quetiapine is highly metabolized. Approximately 73% and 20% of the dose was recovered in the urine and feces, respectively. The average dose fraction of free quetiapine and its major active metabolite is <5% excreted in the urine.

Quetiapine is extensively metabolized by the liver. The major metabolic pathways are sulfoxidation to the sulfoxide metabolite and oxidation to the parent acid metabolite; both metabolites are pharmacologically inactive. In vitro studies using human liver microsomes revealed that the cytochrome P450 3A4 isoenzyme is involved in the metabolism of quetiapine to its major, but inactive, sulfoxide metabolite and in the metabolism of its active metabolite norquetiapine.

Age

Oral clearance of quetiapine was reduced by 40% in elderly patients (≥65 years, n=9) compared to young patients (n=12), and dosing adjustment may be necessary [see Dosage and Administration (2.3)].

Gender

There is no gender effect on the pharmacokinetics of quetiapine.

Race

There is no race effect on the pharmacokinetics of quetiapine.

Smoking

Smoking has no effect on the oral clearance of quetiapine.

Renal Insufficiency

Patients with severe renal impairment (CLcr=10-30 mL/min/1.73m^2, n=8) had a 25% lower mean oral clearance than normal subjects (CLcr>80 mL/min/1.73m^2, n=8), but plasma quetiapine concentrations in the subjects with renal insufficiency were within the range of concentrations seen in normal subjects receiving the same dose. Dosage adjustment is therefore not needed in these patients [see Use in Specific Populations (8.6)].

Hepatic Insufficiency

Hepatically impaired patients (n=8) had a 30% lower mean oral clearance of quetiapine than normal subjects. In 2 of the 8 hepatically impaired patients, AUC and Cmax were 3 times higher than those observed typically in healthy subjects. Since quetiapine is extensively metabolized by the liver, higher plasma levels are expected in the hepatically impaired population, and dosage adjustment may be needed [see Dosage and Administration (2.4) and Use in Specific Populations (8.7)].

Drug-Drug Interaction Studies

The in vivo assessments of effect of other drugs on the pharmacokinetics of quetiapine are summarized in Table 24 [see Dosage and Administration (2.5, 2.6) and Drug Interactions (7.1)].

Table 24: The Effect of Other Drugs on the Pharmacokinetics of Quetiapine
Coadministered; Drug | Dose Schedules |  | Effect on; Quetiapine; Pharmacokinetics
Coadministered; Drug | Coadministered; Drug | Quetiapine | Effect on; Quetiapine; Pharmacokinetics
Phenytoin | 100 mg three times daily | 250 mg three times daily | 5-fold increase in oral clearance
Divalproex | 500 mg twice daily | 150 mg twice daily | 17% increase mean max plasma concentration at steady state.; No effect on absorption or mean oral clearance
Thioridazine | 200 mg twice daily | 300 mg twice daily | 65% increase in oral clearance
Cimetidine | 400 mg three times daily for 4 days | 150 mg three times daily | 20% decrease in mean oral clearance
Ketoconazole (potent CYP 3A4 inhibitor) | 200 mg once daily for 4 days | 25 mg single dose | 84% decrease in oral clearance resulting in a 6.2-fold increase in AUC of quetiapine
Fluoxetine | 60 mg once daily | 300 mg twice daily | No change in steady state PK
Imipramine | 75 mg twice daily | 300 mg twice daily | No change in steady state PK
Haloperidol | 7.5 mg twice daily | 300 mg twice daily | No change in steady state PK
Risperidone | 3 mg twice daily | 300 mg twice daily | No change in steady state PK

In vitro enzyme inhibition data suggest that quetiapine and 9 of its metabolites would have little inhibitory effect on in vivo metabolism mediated by cytochromes CYP 1A2, 2C9, 2C19, 2D6, and 3A4. Quetiapine at doses of 750 mg/day did not affect the single dose pharmacokinetics of antipyrine, lithium or lorazepam (Table 25) [see Drug Interactions (7.2)].

Table 25: The Effect of Quetiapine on the Pharmacokinetics of Other Drugs
Coadministered Drug | Dose Schedules |  | Effect on Other Drugs Pharmacokinetics
Coadministered Drug | Coadministered Drug | Quetiapine | Effect on Other Drugs Pharmacokinetics
Lorazepam | 2 mg, single dose | 250 mg three times daily | Oral clearance of lorazepam reduced by 20%
Divalproex | 500 mg twice daily | 150 mg twice daily | Cmax and AUC of free valproic acid at steady-state was decreased by 10-12%
Lithium | Up to 2400 mg/day given in twice daily doses | 250 mg three times daily | No effect on steady-state pharmacokinetics of lithium
Antipyrine | 1 g, single dose | 250 mg three times daily | No effect on clearance of antipyrine or urinary recovery of its metabolites

13 NONCLINICAL TOXICOLOGY

13.1 Carcinogenesis, Mutagenesis, Impairment of Fertility

Carcinogenesis

Carcinogenicity studies were conducted in C57BL mice and Wistar rats. Quetiapine was administered in the diet to mice at doses of 20, 75, 250, and 750 mg/kg and to rats by gavage at doses of 25, 75, and 250 mg/kg for two years. These doses are equivalent to 0.1, 0.5, 1.5, and 4.5 times the MRHD of 800 mg/day based on mg/m^2 body surface area (mice) or 0.3, 1, and 3 times the MRHD based on mg/m^2 body surface area (rats). There were statistically significant increases in thyroid gland follicular adenomas in male mice at doses 1.5 and 4.5 times the MRHD based on mg/m^2 body surface area and in male rats at a dose of 3 times the MRHD on mg/m^2 body surface area. Mammary gland adenocarcinomas were statistically significantly increased in female rats at all doses tested (0.3, 1, and 3 times the MRHD based on mg/m^2 body surface area).

Thyroid follicular cell adenomas may have resulted from chronic stimulation of the thyroid gland by thyroid stimulating hormone (TSH) resulting from enhanced metabolism and clearance of thyroxine by rodent liver. Changes in TSH, thyroxine, and thyroxine clearance consistent with this mechanism were observed in subchronic toxicity studies in rat and mouse and in a 1-year toxicity study in rat; however, the results of these studies were not definitive. The relevance of the increases in thyroid follicular cell adenomas to human risk, through whatever mechanism, is unknown.

Antipsychotic drugs have been shown to chronically elevate prolactin levels in rodents. Serum measurements in a 1-year toxicity study showed that quetiapine increased median serum prolactin levels a maximum of 32- and 13-fold in male and female rats, respectively. Increases in mammary neoplasms have been found in rodents after chronic administration of other antipsychotic drugs and are considered to be prolactin-mediated. The relevance of this increased incidence of prolactin-mediated mammary gland tumors in rats to human risk is unknown [see Warnings and Precautions (5.15)].

Mutagenesis

Quetiapine was not mutagenic or clastogenic in standard genotoxicity tests. The mutagenic potential of quetiapine was tested in the in vitro Ames bacterial gene mutation assay and in the in vitro mammalian gene mutation assay in Chinese Hamster Ovary cells. The clastogenic potential of quetiapine was tested in the in vitro chromosomal aberration assay in cultured human lymphocytes and in the in vivo bone marrow micronucleus assay in rats up to 500 mg/kg which is 6 times the MRHD based on mg/m^2 body surface area.

Impairment of Fertility

Quetiapine decreased mating and fertility in male Sprague-Dawley rats at oral doses of 50 and 150 mg/kg or approximately 1 and 3 times the MRHD of 800 mg/day based on mg/m^2 body surface area. Drug-related effects included increases in interval to mate and in the number of matings required for successful impregnation. These effects continued to be observed at 3 times the MRHD even after a two-week period without treatment. The no-effect dose for impaired mating and fertility in male rats was 25 mg/kg, or 0.3 times the MRHD based on mg/m^2 body surface area. Quetiapine adversely affected mating and fertility in female Sprague-Dawley rats at an oral dose approximately 1 times the MRHD of 800 mg/day based on mg/m^2 body surface area. Drug-related effects included decreases in matings and in matings resulting in pregnancy, and an increase in the interval to mate. An increase in irregular estrus cycles was observed at doses of 10 and 50 mg/kg, or approximately 0.1 and 1 times the MRHD of 800 mg/day based on mg/m^2 body surface area. The no-effect dose in female rats was 1 mg/kg, or 0.01 times the MRHD of 800 mg/day based on mg/m^2 body surface area.

13.2 Animal Toxicology and/or Pharmacology

Quetiapine caused a dose-related increase in pigment deposition in thyroid gland in rat toxicity studies which were 4 weeks in duration or longer and in a mouse 2-year carcinogenicity study. Doses were 10, 25, 50, 75, 150 and 250 mg/kg in rat studies which are approximately 0.1, 0.3, 0.6, 1, 2 and 3-times the MRHD of 800 mg/day based on mg/m2 body surface area, respectively. Doses in the mouse carcinogenicity study were 20, 75, 250 and 750 mg/kg which are approximately 0.1, 0.5, 1.5, and 4.5 times the MRHD of 800 mg/day based on mg/m2 body surface area. Pigment deposition was shown to be irreversible in rats. The identity of the pigment could not be determined, but was found to be co-localized with quetiapine in thyroid gland follicular epithelial cells. The functional effects and the relevance of this finding to human risk are unknown.

In dogs receiving quetiapine for 6 or 12 months, but not for 1-month, focal triangular cataracts occurred at the junction of posterior sutures in the outer cortex of the lens at a dose of 100 mg/kg, or 4 times the MRHD of 800 mg/day based on mg/m^2 body surface area. This finding may be due to inhibition of cholesterol biosynthesis by quetiapine. Quetiapine caused a dose-related reduction in plasma cholesterol levels in repeat-dose dog and monkey studies; however, there was no correlation between plasma cholesterol and the presence of cataracts in individual dogs. The appearance of delta-8-cholestanol in plasma is consistent with inhibition of a late stage in cholesterol biosynthesis in these species. There also was a 25% reduction in cholesterol content of the outer cortex of the lens observed in a special study in quetiapine treated female dogs. Drug-related cataracts have not been seen in any other species; however, in a 1-year study in monkeys, a striated appearance of the anterior lens surface was detected in 2/7 females at a dose of 225 mg/kg or 5.5 times the MRHD of 800 mg/day based on mg/m^2 body surface area.

14 CLINICAL STUDIES

14.1 Schizophrenia

Short-term Trials - Adults

The efficacy of SEROQUEL XR in the treatment of schizophrenia was demonstrated in 1 short-term, 6-week, fixed-dose, placebo-controlled trial of inpatients and outpatients with schizophrenia (n=573) who met DSM-IV criteria for schizophrenia. SEROQUEL XR (once daily) was administered as 300 mg on Day 1, and the dose was increased to either 400 mg or 600 mg by Day 2, or 800 mg by Day 3. The primary endpoint was the change from baseline of the Positive and Negative Syndrome Scale (PANSS) total score at the end of treatment (Day 42). SEROQUEL XR doses of 400 mg, 600 mg and 800 mg once daily were superior to placebo in the PANSS total score at Day 42 (Study 1 in Table 26).

Short-term Trials -Adolescents (ages 13-17)

The efficacy of SEROQUEL XR in the treatment of schizophrenia in adolescents (13-17 years of age) was supported by a 6-week, double-blind, placebo-controlled trial. Patients who met DSM-IV diagnostic criteria for schizophrenia were randomized into one of three treatment groups: SEROQUEL 400 mg/day (n=73), SEROQUEL 800 mg/day (n=74), or placebo (n=75). Study medication was initiated at 50 mg/day and on day 2 increased to 100 mg/per day (divided and given two or three times per day). Subsequently, the dose was titrated to the target dose of 400 mg/day or 800 mg/day using increments of 100 mg/day, divided and given two or three times daily. The primary efficacy variable was the mean change from baseline in total Positive and Negative Syndrome Scale (PANSS). SEROQUEL at 400 mg/day and 800 mg/day was superior to placebo in the reduction of PANSS total score (Study 2 in Table 26).

Table 26: Schizophrenia Short-Term Trials
Study; Number | Treatment Group | Primary Efficacy Endpoint: PANSS Total
Study; Number | Treatment Group | Mean Baseline Score (SD) | LS Mean Change from Baseline (SE) | Placebo-subtracted Difference [Difference (drug minus placebo) in least-squares mean change from baseline] (95% CI)
Study 1 | SEROQUEL XR (400 mg/day) [Doses that are statistically significantly superior to placebo] | 95.8 (13.9) | -24.8 (2.5) | -6.1 (-11.5, -0.6)
Study 1 | SEROQUEL XR (600 mg/day) | 96.8 (14.1) | -30.9 (2.5) | -12.1 (-17.6, -6.7)
Study 1 | SEROQUEL XR (800 mg/day) | 97.3 (14.7) | -31.3 (2.5) | -12.5 (-17.9, -7.1)
Study 1 | SEROQUEL (400 mg/day), [Included in the trial for assay sensitivity] | 96.5 (16.0) | -26.6 (2.4) | -7.8 (-13.1, -2.4)
Study 1 | Placebo | 96.2 (13.3) | -18.8 (2.5) | --
Study 2; (adolescents) | SEROQUEL (400 mg/day) | 96.2 (17.7) | -27.3 (2.6) | -8.2 (-16.1, -0.3)
Study 2; (adolescents) | SEROQUEL (800 mg/day) | 96.9 (15.3) | -28.4 (1.8) | -9.3 (-16.2, -2.4)
Study 2; (adolescents) | Placebo | 96.2 (17.7) | -19.2 (3.0)
SD: standard deviation; SE: standard error; LS Mean: least-squares mean; CI: unadjusted confidence interval.

Maintenance Trials

In a longer-term trial (Study 3), clinically stable adult outpatients (n=171) meeting DSM-IV criteria for schizophrenia who remained stable following 16 weeks of open-label treatment with flexible doses of SEROQUEL XR (400 mg/day-800 mg/day) were randomized to placebo or to continue on their current SEROQUEL XR (400 mg/day-800 mg/day) for observation for possible relapse during the double-blind continuation (maintenance) phase. Stabilization during the open-label phase was defined as receiving a stable dose of SEROQUEL XR and having a CGI-S≤4 and a PANSS score ≤60 from beginning to end of this open-label phase (with no increase of ≥10 points in PANSS total score). Relapse during the double-blind phase was defined in terms of a ≥30% increase in the PANSS Total score, or CGI-Improvement score of ≥6, or hospitalization due to worsening of schizophrenia, or need for any other antipsychotic medication. Patients on SEROQUEL XR experienced a statistically significant longer time to relapse than did patients on placebo (Figure 1).

Figure 1: Kaplan-Meier Curves of Time to Schizophrenic Relapse (Study 3)

PLA Placebo. QTP Quetiapine. XR Extended-release.

Note: Results are from the interim analysis.

14.2 Bipolar Disorder

Bipolar I Disorder, manic or mixed episodes

Adults

The efficacy of SEROQUEL XR in the acute treatment of manic episodes was established in one 3-week, placebo-controlled trial (Study 1 in Table 27) in patients who met DSM-IV criteria for bipolar I disorder with manic or mixed episodes with or without psychotic features (N=316). Patients were hospitalized for a minimum of 4 days at randomization. Patients randomized to SEROQUEL XR received 300 mg on Day 1 and 600 mg on Day 2. Afterwards, the dose could be adjusted between 400 mg and 800 mg per day.

The primary rating instrument used for assessing manic symptoms in these trials was the Young Mania Rating Scale (YMRS), an 11-item clinician-rated scale traditionally used to assess the degree of manic symptoms in a range from 0 (no manic features) to 60 (maximum score). SEROQUEL XR was superior to placebo in the reduction of the YMRS total score at week 3.

The efficacy of SEROQUEL in the treatment of acute manic episodes was also established in 3 placebo-controlled trials in patients who met DSM-IV criteria for bipolar I disorder with manic episodes. These trials included patients with or without psychotic features and excluded patients with rapid cycling and mixed episodes. Of these trials, 2 were monotherapy (12 weeks) and 1 was adjunct therapy (3 weeks) to either lithium or divalproex. Key outcomes in these trials were change from baseline in the YMRS score at 3 and 12 weeks for monotherapy and at 3 weeks for adjunct therapy. Adjunct therapy is defined as the simultaneous initiation or subsequent administration of SEROQUEL with lithium or divalproex.

The results of the trials follow:

Monotherapy

In two 12-week trials (n=300, n=299) comparing SEROQUEL to placebo, SEROQUEL was superior to placebo in the reduction of the YMRS total score at weeks 3 and 12. The majority of patients in these trials taking SEROQUEL were dosed in a range between 400 mg/day and 800 mg/ day (Studies 2 and 3 in Table 27).

Adjunct Therapy

In a 3-week placebo-controlled trial, 170 patients with bipolar mania (YMRS ≥20) were randomized to receive SEROQUEL or placebo as adjunct treatment to lithium or divalproex. Patients may or may not have received an adequate treatment course of lithium or divalproex prior to randomization. SEROQUEL was superior to placebo when added to lithium or divalproex alone in the reduction of YMRS total score. The majority of patients in this trial taking SEROQUEL were dosed in a range between 400 mg/day and 800 mg/day (Study 4 in Table 27).

Children and Adolescents (ages 10-17)

The efficacy of SEROQUEL XR in the acute treatment of manic episodes associated with bipolar I disorder in children and adolescents (10 - 17 years of age) was extrapolated from a 3-week, double-blind, placebo-controlled, multicenter trial. Patients who met DSM-IV diagnostic criteria for a manic episode were randomized into one of three treatment groups: SEROQUEL 400 mg/day (n=95), SEROQUEL 600 mg/day (n=98), or placebo (n=91). Study medication was initiated at 50 mg/day and on day 2 increased to 100 mg/day (divided doses given two or three times daily). Subsequently, the dose was titrated to a target dose of 400 mg/day or 600 mg/day using increments of 100 mg/day, given in divided doses two or three times daily. The primary efficacy variable was the mean change from baseline in total YMRS score. SEROQUEL 400 mg/day and 600 mg/day were superior to placebo in the reduction of YMRS total score (Study 5 in Table 27).

Table 27: Mania Trials
Study Number | Treatment Group | Primary Efficacy Measure: YMRS Total
Study Number | Treatment Group | Mean Baseline Score (SD) [Adult data mean baseline score is based on patients included in the primary analysis; pediatric mean baseline score is based on all patients in the ITT population.] | LS Mean Change from Baseline (SE) | Placebo-subtracted Difference [Difference (drug minus placebo) in least-squares mean change from baseline.]; (95% CI)
Study 1 | SEROQUEL XR (400-800 mg/day) [Doses that are statistically significantly superior to placebo.] | 28.8 (5.4) | -14.3 (0.9) | -3.8 (-5.7, -2.0)
Study 1 | Placebo | 28.4 (5.1) | -10.5 (0.9) | --
Study 2 | SEROQUEL (200-800 mg/day) | 34.0 (6.1) | -12.3 (1.3) | -4.0 (-7.0, -1.0)
Study 2 | Haloperidol [Included in the trial as an active comparator.] | 32.3 (6.0) | -15.7 (1.3) | -7.4 (-10.4, -4.4)
Study 2 | Placebo | 33.1 (6.6) | -8.3 (1.3) | --
Study 3 | SEROQUEL (200-800 mg/day) | 32.7 (6.5) | -14.6 (1.5) | -7.9 (-10.9, -5.0)
Study 3 | Lithium | 33.3 (7.1) | -15.2 (1.6) | -8.5 (-11.5, -5.5)
Study 3 | Placebo + mood stabilizer | 34.0 (6.9) | -6.7 (1.6) | --
Study 4 | SEROQUEL (200-800 mg/day) + mood stabilizer | 31.5 (5.8) | -13.8 (1.6) | -3.8 (-7.1, -0.6)
Study 4 | Placebo + mood stabilizer | 31.1 (5.5) | -10 (1.5) | --
Study 5; (children and adolescents) | SEROQUEL (400 mg/day) | 29.4 (5.9) | -14.3 (0.96) | -5.2 (-8.1, -2.3)
Study 5; (children and adolescents) | SEROQUEL (600 mg/day) | 29.6 (6.4) | -15.6 (0.97) | -6.6 (-9.5, -3.7)
Study 5; (children and adolescents) | Placebo | 30.7 (5.9) | -9.0 (1.1) | --
Mood stabilizer: lithium or divalproex; SD: standard deviation; SE: standard error; LS Mean: least-squares mean; CI: unadjusted confidence interval.

Bipolar Disorder, Depressive Episodes

Adults

The efficacy of SEROQUEL XR for the acute treatment of depressive episodes associated with bipolar disorder in patients who met DSM-IV criteria for bipolar disorder was established in one 8-week, randomized, double-blind, placebo-controlled study (N=280 outpatients). This study included patients with bipolar I and II disorder, and those with and without a rapid cycling course. Patients randomized to SEROQUEL XR were administered 50 mg on Day 1, 100 mg on Day 2, 200 mg on Day 3, and 300 mg on Day 4 and after.

The primary rating instrument used to assess depressive symptoms was the Montgomery-Asberg Depression Rating Scale (MADRS), a 10-item clinician-rated scale with scores ranging from 0 (no depressive features) to 60 (maximum score). The primary endpoint was the change from baseline in MADRS score at week 8. SEROQUEL XR was superior to placebo in reduction of MADRS score at week 8 (Study 6 in Table 28).

The efficacy of SEROQUEL for the treatment of depressive episodes associated with bipolar disorder was established in 2 identical 8-week, randomized, double-blind, placebo-controlled studies (N=1045). These studies included patients with either bipolar I or II disorder and those with or without a rapid cycling course. Patients randomized to SEROQUEL were administered fixed doses of either 300 mg or 600 mg once daily.

The primary rating instrument used to assess depressive symptoms in these studies was the MADRS. The primary endpoint in both studies was the change from baseline in MADRS score at week 8. In both studies, SEROQUEL was superior to placebo in reduction of MADRS score at week 8 (Studies 7 and 8 in Table 28). In these studies, no additional benefit was seen with the 600 mg dose. For the 300 mg dose group, statistically significant improvements over placebo were seen in overall quality of life and satisfaction related to various areas of functioning, as measured using the Q-LES-Q(SF).

Table 28: Depressive Episodes Associated with Bipolar Disorder
Study Number | Treatment Group | Primary Efficacy Measure: MADRS Total
Study Number | Treatment Group | Mean Baseline Score (SD) | LS Mean Change from Baseline (SE) | Placebo-subtracted Difference [Difference (drug minus placebo) in least-squares mean change from baseline.] (95% CI)
Study 6 | SEROQUEL XR (300 mg/day) [Doses that are statistically significantly superior to placebo.] | 29.8 (5.2) | -17.4 (1.2) | -5.5 (-7.9, -3.2)
 | Placebo | 30.1 (5.5) | -11.9 (1.2) | --
Study 7 | SEROQUEL (300 mg/day) | 30.3 (5.0) | -16.4 (0.9) | -6.1 (-8.3, -3.9)
 | SEROQUEL (600 mg/day) | 30.3 (5.3) | -16.7 (0.9) | -6.5 (-8.7, -4.3)
 | Placebo | 30.6 (5.3) | -10.3 (0.9) | --
Study 8 | SEROQUEL (300 mg/day) | 31.1 (5.7) | -16.9 (1.0) | -5.0 (-7.3, -2.7)
 | SEROQUEL (600 mg/day) | 29.9 (5.6) | -16.0 (1.0) | -4.1 (-6.4, -1.8)
 | Placebo | 29.6 (5.4) | -11.9 (1.0) | --
SD: standard deviation; SE: standard error; LS Mean: least-squares mean; CI: unadjusted confidence interval.

Maintenance Treatment as an Adjunct to Lithium or Divalproex

The efficacy of SEROQUEL in the maintenance treatment of bipolar I disorder was established in 2 placebo-controlled trials in patients (n=1326) who met DSM-IV criteria for bipolar I disorder (studies 9 and 10). The trials included patients whose most recent episode was manic, depressed, or mixed, with or without psychotic features. In the open-label phase, patients were required to be stable on SEROQUEL plus lithium or divalproex for at least 12 weeks in order to be randomized. On average, patients were stabilized for 15 weeks. In the randomization phase, patients continued treatment with lithium or divalproex and were randomized to receive either SEROQUEL (administered twice-daily totaling 400 mg/day to 800 mg/day) or placebo. Approximately 50% of the patients had discontinued from the SEROQUEL group by day 280 and 50% of the placebo group had discontinued by day 117 of double-blind treatment. The primary endpoint in these studies was time to recurrence of a mood event (manic, mixed, or depressed episode). A mood event was defined as medication initiation or hospitalization for a mood episode; YMRS score ≥20 or MADRS score ≥20 at 2 consecutive assessments; or study discontinuation due to a mood event.

In both studies, SEROQUEL was superior to placebo in increasing the time to recurrence of any mood event (Figure 2 and Figure 3). The treatment effect was present for increasing time to recurrence of both manic and depressed episodes. The effect of SEROQUEL was independent of any specific subgroup (assigned mood stabilizer, sex, age, race, most recent bipolar episode, or rapid cycling course).

Figure 2: Kaplan-Meier Curves of Time to Recurrence of a Mood Event (Study 9)

Figure 3: Kaplan-Meier Curves of Time to Recurrence of a Mood Event (Study 10)

14.3 Major Depressive Disorder, Adjunctive Therapy to Antidepressants

The efficacy of SEROQUEL XR as adjunctive therapy to antidepressants in the treatment of MDD was demonstrated in two 6-week placebo-controlled, fixed-dose trials (n=936). SEROQUEL XR 150 mg/day or 300 mg/day was given as adjunctive therapy to existing antidepressant therapy in patients who had previously shown an inadequate response to at least one antidepressant. SEROQUEL XR was administered as 50 mg/day on Days 1 and 2, and increased to 150 mg/day on Day 3 for both dose groups. On Day 5, the dose was increased to 300 mg/day in the 300 mg/day fixed-dose group. Inadequate response was defined as having continued depressive symptoms for the current episode [Hamilton Depression Rating Scale (HAM-D) total score of ≥20] despite using an antidepressant for 6 weeks at or above the minimally effective labelled dose. The mean HAM-D total score at entry was 24, and 17% of patients scored 28 or greater. Patients were on various antidepressants prior to study entry including SSRI’s (paroxetine, fluoxetine, sertraline, escitalopram, or citalopram), SNRI’s, (duloxetine and venlafaxine,) TCA (amitriptyline), and other (bupropion).

The primary endpoint in these trials was change from baseline to week 6 in the Montgomery-Asberg Depression Rating Scale (MADRS.), SEROQUEL XR 300 mg once daily as adjunctive treatment to other antidepressant therapy was superior to antidepressant alone in reduction of MADRS total score in both trials. SEROQUEL XR 150 mg once daily as adjunctive treatment was superior to antidepressant therapy alone in reduction of MADRS total score in one trial (studies 1 and 2 in Table 29).

Table 29: Major Depressive Disorder, Adjunctive Therapy to Antidepressants
Study Number | Treatment Group | Primary Efficacy Measure: MADRS Total
Study Number | Treatment Group | Mean Baseline Score (SD) | LS Mean Change from Baseline (SE) | Placebo-subtracted Difference [Difference (drug minus placebo) in least-squares mean change from baseline.] (95% CI)
Study 1 | SEROQUEL XR (150 mg/day) + AD | 27.2 (5.2) | -13.6 (0.8) | -1.9 (-3.9, 0.1)
 | SEROQUEL XR (300 mg/day) [Doses that are statistically significantly superior to placebo.] + AD | 27.6 (5.0) | -14.7 (0.8) | -3.0 (-5.0, -1.0)
 | Placebo + AD | 27.6 (5.5) | -11.7 (0.8) | --
Study 2 | SEROQUEL XR (150 mg/day) + AD | 28.6 (5.4) | -15.3 (0.7) | -3.1 (-4.9, -1.2)
 | SEROQUEL XR (300 mg/day) + AD | 28.4 (5.5) | -14.9 (0.7) | -2.7 (-4.6, -0.8)
 | Placebo | 28.2 (5.6) | -12.2 (0.7) | --
AD: Antidepressant; SD: standard deviation; SE: standard error; LS Mean: least-squares mean; CI: unadjusted confidence interval.

16 HOW SUPPLIED/STORAGE AND HANDLING

• 50 mg Tablets (NDC 61269-270-60) peach, film-coated, capsule-shaped, biconvex, intagliated tablet with “XR 50” on one side and plain on the other are supplied in bottles of 60 tablets.

• 150 mg Tablets (NDC 61269-271-60) white, film-coated, capsule-shaped, biconvex, intagliated tablet with “XR 150” on one side and plain on the other are supplied in bottles of 60 tablets.

• 200 mg Tablets (NDC 61269-272-60) yellow, film-coated, capsule-shaped, biconvex, intagliated tablet with “XR 200” on one side and plain on the other are supplied in bottles of 60 tablets.

• 300 mg Tablets (NDC 61269-273-60) pale yellow, film-coated, capsule-shaped, biconvex, intagliated tablet with “XR 300” on one side and plain on the other are supplied in bottles of 60 tablets.

• 400 mg Tablets (NDC 61269-274-60) white, film-coated, capsule-shaped, biconvex, intagliated tablet with “XR 400” on one side and plain on the other are supplied in bottles of 60 tablets.

Store SEROQUEL XR at 25ºC (77ºF); excursions permitted to 15-30ºC (59-86ºF) [See USP].

17 PATIENT COUNSELING INFORMATION

Advise the patient to read the FDA-approved patient labeling (Medication Guide).

Patients should be advised of the following issues and asked to alert their prescriber if these occur while taking SEROQUEL XR.

Increased Mortality in Elderly Patients with Dementia-Related Psychosis

Patients and caregivers should be advised that elderly patients with dementia-related psychoses treated with atypical antipsychotic drugs are at increased risk of death compared with placebo. SEROQUEL XR is not approved for elderly patients with dementia-related psychosis [see Warnings and Precautions (5.1)].

Suicidal Thoughts and Behaviors

Patients, their families, and their caregivers should be encouraged to be alert to the emergence of anxiety, agitation, panic attacks, insomnia, irritability, hostility, aggressiveness, impulsivity, akathisia (psychomotor restlessness), hypomania, mania, other unusual changes in behavior, worsening of depression, and suicidal ideation, especially early during antidepressant treatment and when the dose is adjusted up or down. Families and caregivers of patients should be advised to look for the emergence of such symptoms on a day-to-day basis, since changes may be abrupt. Such symptoms should be reported to the patient's prescriber or health professional, especially if they are severe, abrupt in onset, or were not part of the patient's presenting symptoms. Symptoms such as these may be associated with an increased risk for suicidal thinking and behavior and indicate a need for very close monitoring and possibly changes in the medication [see Warnings and Precautions (5.2)].

Neuroleptic Malignant Syndrome (NMS)

Patients should be advised to report to their physician any signs or symptoms that may be related to NMS. These may include muscle stiffness and high fever [see Warnings and Precautions (5.4)].

Hyperglycemia and Diabetes Mellitus

Patients should be aware of the symptoms of hyperglycemia (high blood sugar) and diabetes mellitus. Patients who are diagnosed with diabetes, those with risk factors for diabetes, or those that develop these symptoms during treatment should have their blood glucose monitored at the beginning of and periodically during treatment [see Warnings and Precautions (5.5)].

Hyperlipidemia

Patients should be advised that elevations in total cholesterol, LDL-cholesterol and triglycerides and decreases in HDL-cholesterol may occur. Patients should have their lipid profile monitored at the beginning of and periodically during treatment [see Warnings and Precautions (5.5)].

Weight Gain

Patients should be advised that they may experience weight gain. Patients should have their weight monitored regularly [see Warnings and Precautions (5.5)].

Orthostatic Hypotension

Patients should be advised of the risk of orthostatic hypotension (symptoms include feeling dizzy or lightheaded upon standing, which may lead to falls) especially during the period of initial dose titration, and also at times of re-initiating treatment or increases in dose [see Warnings and Precautions (5.7)].

Increased Blood Pressure in Children and Adolescents

Children and adolescent patients should have their blood pressure measured at the beginning of, and periodically during, treatment [see Warnings and Precautions (5.9)].

Leukopenia/Neutropenia

Patients with a pre-existing low WBC or a history of drug induced leukopenia/neutropenia should be advised that they should have their CBC monitored while taking SEROQUEL XR. Patients should be advised to talk to their doctor as soon as possible if they have a fever, flu-like symptoms, sore throat, or any other infection as this could be a result of a very low WBC, which may require SEROQUEL XR to be stopped and/or treatment to be given [see Warnings and Precautions (5.10)].

Interference with Cognitive and Motor Performance

Patients should be advised of the risk of somnolence or sedation (which may lead to falls), especially during the period of initial dose titration. Patients should be cautioned about performing any activity requiring mental alertness, such as operating a motor vehicle (including automobiles) or operating machinery, until they are reasonably certain quetiapine therapy does not affect them adversely [see Warnings and Precautions (5.16)].

Heat Exposure and Dehydration

Patients should be advised regarding appropriate care in avoiding overheating and dehydration [see Warnings and Precautions (5.17)].

Concomitant Medication

As with other medications, patients should be advised to notify their physicians if they are taking, or plan to take, any prescription or over-the-counter drugs [see Drug Interactions (7.1)].

Pregnancy

Advise pregnant women to notify their healthcare provider if they become pregnant or intend to become pregnant during treatment with SEROQUEL XR. Advise patients that SEROQUEL XR may cause extrapyramidal and/or withdrawal symptoms (agitation, hypertonia, hypotonia, tremor, somnolence, respiratory distress, and feeding disorder) in a neonate. Advise patients that there is a pregnancy registry that monitors pregnancy outcomes in women exposed to SEROQUEL XR during pregnancy [see Use in Specific Populations (8.1)].

Infertility

Advise females of reproductive potential that SEROQUEL XR may impair fertility due to an increase in serum prolactin levels. The effects on fertility are reversible [see Use in Specific Populations (8.3)].

Need for Comprehensive Treatment Program

SEROQUEL XR is indicated as an integral part of a total treatment program for adolescents with schizophrenia and pediatric bipolar disorder that may include other measures (psychological, educational, and social). Effectiveness and safety of SEROQUEL XR have not been established in pediatric patients less than 13 years of age for schizophrenia or less than 10 years of age for bipolar mania. Appropriate educational placement is essential and psychosocial intervention is often helpful. The decision to prescribe atypical antipsychotic medication will depend upon the physician’s assessment of the chronicity and severity of the patient’s symptoms [see Indications and Usage (1.4)].

Medication Guide

SEROQUEL XR (SER-oh-kwell X-R)

(quetiapine)

Extended-Release Tablets

Read this Medication Guide before you start taking SEROQUEL XR and each time you get a refill. There may be new information. This Medication Guide does not take the place of talking to your healthcare provider about your medical condition or treatment.

What is the most important information I should know about SEROQUEL XR?

SEROQUEL XR may cause serious side effects, including:

1.risk of death in the elderly with dementia: Medicines like SEROQUEL XR can increase the risk of death in elderly people who have memory loss (dementia). SEROQUEL XR is not for treating psychosis in the elderly with dementia.2.risk of suicidal thoughts or actions (antidepressant medicines, depression and other serious mental illnesses, and suicidal thoughts or actions).

Talk to your or your family member’s, healthcare provider about:

∘all risks and benefits of treatment with antidepressant medicines∘all treatment choices for depression or other serious mental illness

•Antidepressant medicines may increase suicidal thoughts or actions in some children, teenagers, and young adults within the first few months of treatment.•Depression and other serious mental illnesses are the most important causes of suicidal thoughts and actions. Some people may have a particularly high risk of having suicidal thoughts or actions. These include people who have (or have a family history of) depression, bipolar illness (also called manic-depressive illness), or suicidal thoughts or actions.•How can I watch for and try to prevent suicidal thoughts and actions in myself or a family member?∘Pay close attention to any changes, especially sudden changes, in mood, behaviors, thoughts, or feelings. This is very important when an antidepressant medicine is started or when the dose is changed.∘Call the healthcare provider right away to report new or sudden changes in mood, behavior, thoughts, or feelings.∘Keep all follow-up visits with the healthcare provider as scheduled. Call the healthcare provider between visits as needed, especially if you have concerns about symptoms.

Call a healthcare provider right away if you or your family member has any of the following symptoms, especially if they are new, worse, or worry you:

•thoughts about suicide or dying•attempts to commit suicide•new or worse depression•new or worse anxiety•feeling very agitated or restless•panic attacks•trouble sleeping (insomnia)•new or worse irritability•acting aggressive, being angry, or violent•acting on dangerous impulses•an extreme increase in activity and talking (mania)•other unusual changes in behavior or mood

What else do I need to know about antidepressant medicines?

•Never stop an antidepressant medicine without first talking to your healthcare provider. Stopping an antidepressant medicine suddenly can cause other symptoms.•Antidepressants are medicines used to treat depression and other illnesses. It is important to discuss all the risks of treating depression, and also the risks of not treating it. Patients and their families or other caregivers should discuss all treatment choices with the healthcare provider, not just the use of antidepressants.•Antidepressant medicines have other side effects. Talk to the healthcare provider about the side effects of the medicine prescribed for you or your family member.•Antidepressant medicines can interact with other medicines. Know all of the medicines that you or your family member take. Keep a list of all medicines to show the healthcare provider. Do not start new medicines without first checking with your healthcare provider.•Not all antidepressant medicines prescribed for children are FDA approved for use in children.Talk to your child’s healthcare provider for more information.

What is SEROQUEL XR?

SEROQUEL XR is a prescription medicine used to treat:

•schizophrenia in people 13 years of age or older•bipolar disorder in adults, including:∘depressive episodes associated with bipolar disorder∘manic episodes associated with bipolar I disorder alone or with lithium or divalproex∘long-term treatment of bipolar I disorder with lithium or divalproex•manic episodes associated with bipolar I disorder in children ages 10 to 17 years old•major depressive disorder as add-on treatment with antidepressant medicines when your healthcare provider determines that 1 antidepressant alone is not enough to treat your depression.

It is not known if SEROQUEL XR is safe and effective in children under 10 years of age.

Who should not take SEROQUEL XR?

Do not take SEROQUEL XR if you are allergic to quetiapine or any of the ingredients in SEROQUEL XR. See the end of this Medication Guide for a complete list of ingredients in SEROQUEL XR.

What should I tell my healthcare provider before taking SEROQUEL XR?

Before you take SEROQUEL XR, tell your healthcare provider if you have or have had:

•diabetes or high blood sugar in you or your family. Your healthcare provider should check your blood sugar before you start SEROQUEL XR and also during therapy.•high levels of total cholesterol, triglycerides or LDL-cholesterol or low levels of HDL-cholesterol•low or high blood pressure•low white blood cell count•cataracts•seizures•abnormal thyroid tests•high prolactin levels•heart problems•liver problems•any other medical condition•pregnancy or plans to become pregnant. It is not known if SEROQUEL XR will harm your unborn baby.•If you become pregnant while receiving SEROQUEL XR, talk to your healthcare provider about registering with the National Pregnancy Registry for Atypical Antipsychotics. You can register by calling 1-866-961-2388 or go to http://womensmentalhealth.org/clinical-and-research-programs/pregnancyregistry/•breast-feeding or plans to breast-feed. SEROQUEL XR can pass into your breast milk. Talk to your healthcare provider about the best way to feed your baby if you receive SEROQUEL XR.•if you have or have had a condition where you cannot completely empty your bladder (urinary retention), have an enlarged prostate, or constipation, or increased pressure inside your eyes.

Tell the healthcare provider about all the medicines that you take or recently have taken including prescription medicines, over-the-counter medicines, herbal supplements and vitamins.

SEROQUEL XR and other medicines may affect each other causing serious side effects. SEROQUEL XR may affect the way other medicines work, and other medicines may affect how SEROQUEL XR works.

Tell your healthcare provider if you are having a urine drug screen because SEROQUEL XR may affect your test results. Tell those giving the test that you are taking SEROQUEL XR.

How should I take SEROQUEL XR?

•Take SEROQUEL XR exactly as your healthcare provider tells you to take it. Do not change the dose yourself.•Take SEROQUEL XR by mouth, with a light meal or without food.•SEROQUEL XR should be swallowed whole and not split, chewed or crushed.•If you feel you need to stop SEROQUEL XR, talk with your healthcare provider first. If you suddenly stop taking SEROQUEL XR, you may have side effects such as trouble sleeping or trouble staying asleep (insomnia), nausea, and vomiting.•If you miss a dose of SEROQUEL XR, take it as soon as you remember. If you are close to your next dose, skip the missed dose. Just take the next dose at your regular time. Do not take 2 doses at the same time unless your healthcare provider tells you to. If you are not sure about your dosing, call your healthcare provider.

What should I avoid while taking SEROQUEL XR?

•Do not drive, operate machinery, or do other dangerous activities until you know how SEROQUEL XR affects you. SEROQUEL XR may make you drowsy.•Avoid getting overheated or dehydrated.∘Do not over-exercise.∘In hot weather, stay inside in a cool place if possible.∘Stay out of the sun. Do not wear too much or heavy clothing.∘Drink plenty of water.•Do not drink alcohol while taking SEROQUEL XR. It may make some side effects of SEROQUEL XR worse.

What are possible side effects of SEROQUEL XR?

SEROQUEL XR can cause serious side effects, including:

See “What is the most important information I should know about SEROQUEL XR?”

•stroke that can lead to death can happen in elderly people with dementia who take medicines like SEROQUEL XR•neuroleptic malignant syndrome (NMS). NMS is a rare but very serious condition that can happen in people who take antipsychotic medicines, including SEROQUEL XR. NMS can cause death and must be treated in a hospital. Call your healthcare provider right away if you become severely ill and have some or all of these symptoms:∘high fever∘excessive sweating∘rigid muscles∘confusion∘changes in your breathing, heartbeat, and blood pressure•falls can happen in some people who take SEROQUEL XR. These falls may cause serious injuries.•high blood sugar (hyperglycemia). High blood sugar can happen if you have diabetes already or if you have never had diabetes. High blood sugar could lead to:∘build up of acid in your blood due to ketones (ketoacidosis)∘coma∘death

Increases in blood sugar can happen in some people who take SEROQUEL XR. Extremely high blood sugar can lead to coma or death. If you have diabetes or risk factors for diabetes (such as being overweight or a family history of diabetes) your healthcare provider should check your blood sugar before you start SEROQUEL XR and during therapy.

Call your healthcare provider if you have any of these symptoms of high blood sugar (hyperglycemia) while taking SEROQUEL XR:

∘feel very thirsty∘need to urinate more than usual∘feel very hungry∘feel weak or tired∘feel sick to your stomach∘feel confused, or your breath smells fruity•high fat levels in your blood (increased cholesterol and triglycerides). High fat levels may happen in people treated with SEROQUEL XR. You may not have any symptoms, so your healthcare provider may decide to check your cholesterol and triglycerides during your treatment with SEROQUEL XR.•increase in weight (weight gain). Weight gain is common in people who take SEROQUEL XR so you and your healthcare provider should check your weight regularly. Talk to your healthcare provider about ways to control weight gain, such as eating a healthy, balanced diet, and exercising.•movements you cannot control in your face, tongue, or other body parts (tardive dyskinesia). These may be signs of a serious condition. Tardive dyskinesia may not go away, even if you stop taking SEROQUEL XR. Tardive dyskinesia may also start after you stop taking SEROQUEL XR.•decreased blood pressure (orthostatic hypotension), including lightheadedness or fainting caused by a sudden change in heart rate and blood pressure when rising too quickly from a sitting or lying position.•increases in blood pressure in children and teenagers. Your healthcare provider should check blood pressure in children and adolescents before starting SEROQUEL XR and during therapy. SEROQUEL XR is not approved for patients under 10 years of age.•low white blood cell count. Tell your healthcare provider as soon as possible if you have a fever, flu-like symptoms, or any other infection, as this could be a result of a very low white blood cell count. Your healthcare provider may check your white blood cell level to determine if further treatment or other action is needed•cataracts•seizures•abnormal thyroid tests: Your healthcare provider may do blood tests to check your thyroid hormone level.•increases in prolactin levels: Your healthcare provider may do blood tests to check your prolactin levels.•sleepiness, drowsiness, feeling tired, difficulty thinking and doing normal activities•increased body temperature•difficulty swallowing•trouble sleeping or trouble staying asleep (insomnia), nausea, or vomiting if you suddenly stop taking SEROQUEL XR. These symptoms usually get better 1 week after you start having them.

The most common side effects of SEROQUEL XR include:

•dry mouth•constipation•dizziness•increased appetite•upset stomach•fatigue•stuffy nose•difficulty moving•disturbance in speech or language

Children and Adolescents:

•drowsiness•dizziness•fatigue•stuffy nose•increased appetite•upset stomach•vomiting•dry mouth•tachycardia•weight increased

These are not all the possible side effects of SEROQUEL XR. For more information, ask your healthcare provider or pharmacist.

Call your doctor for medical advice about side effects. You may report side effects to FDA at 1-800-FDA-1088.

How should I store SEROQUEL XR?

•Store SEROQUEL XR at room temperature, between 68°F to 77°F (20°C to 25°C).•Keep SEROQUEL XR and all medicines out of the reach of children.

General information about the safe and effective use of SEROQUEL XR.

Medicines are sometimes prescribed for purposes other than those listed in a Medication Guide. Do not use SEROQUEL XR for a condition for which it was not prescribed. Do not give SEROQUEL XR to other people, even if they have the same symptoms you have. It may harm them.

This Medication Guide summarizes the most important information about SEROQUEL XR. If you would like more information, talk with your healthcare provider. You can ask your pharmacist or healthcare provider for information about SEROQUEL XR that is written for health professionals.

For more information, go to www.seroquel.com, or call 1-888-864-2308.

What are the ingredients in SEROQUEL XR?

Active ingredient: quetiapine

Inactive ingredients: lactose monohydrate, microcrystalline cellulose, sodium citrate, hypromellose, and magnesium stearate. The film coating for all SEROQUEL XR tablets contain hypromellose, polyethylene glycol 400 and titanium dioxide. In addition, yellow iron oxide (50, 200 and 300 mg tablets) and red iron oxide (50 mg tablets) are included in the film coating of specific strengths.

This Medication Guide has been approved by the U.S. Food and Drug Administration.

Licensed by:
CHEPLAPHARM Arzneimittel GmbH
Ziegelhof 24
17489 Greifswald, Germany
© 2025 CHEPLAPHARM Arzneimittel GmbH. All rights reserved.

Distributed by:

H2-Pharma, LLC
Montgomery, AL 36117, USA

Revised: 04/2025

Package/Label Display Panel - 50 mg

NDC 61269-270-60 60 tablets

SEROQUELXR®

(quetiapine)

extended-release tablets

50 mg*

Medication Guide must be

dispensed to patients.

Once Daily Rx only

CHEPLAPHARM

Package/Label Display Panel - 150 mg

NDC 61269-271-60 60 tablets

SEROQUELXR®

(quetiapine)

extended-release tablets

150 mg*

Medication Guide must be

dispensed to patients.

Once Daily Rx only

CHEPLAPHARM

Package/Label Display Panel - 200 mg

NDC 61269-272-60 60 tablets

SEROQUELXR®

(quetiapine)

extended-release tablets

200 mg*

Rx only

Medication Guide must be

dispensed to patients.

Once Daily

CHEPLAPHARM

Package/Label Display Panel - 300 mg

NDC 61269-273-60 60 tablets

SEROQUELXR®

(quetiapine)

extended-release tablets

300 mg*

Rx only

Medication Guide must be

dispensed to patients.

Once Daily

CHEPLAPHARM

Package/Label Display Panel - 400 mg

NDC 61269-274-60 60 tablets

SEROQUELXR®

(quetiapine)

extended-release tablets

400 mg*

Rx only

Medication Guide must be

dispensed to patients.

Once Daily

CHEPLAPHARM